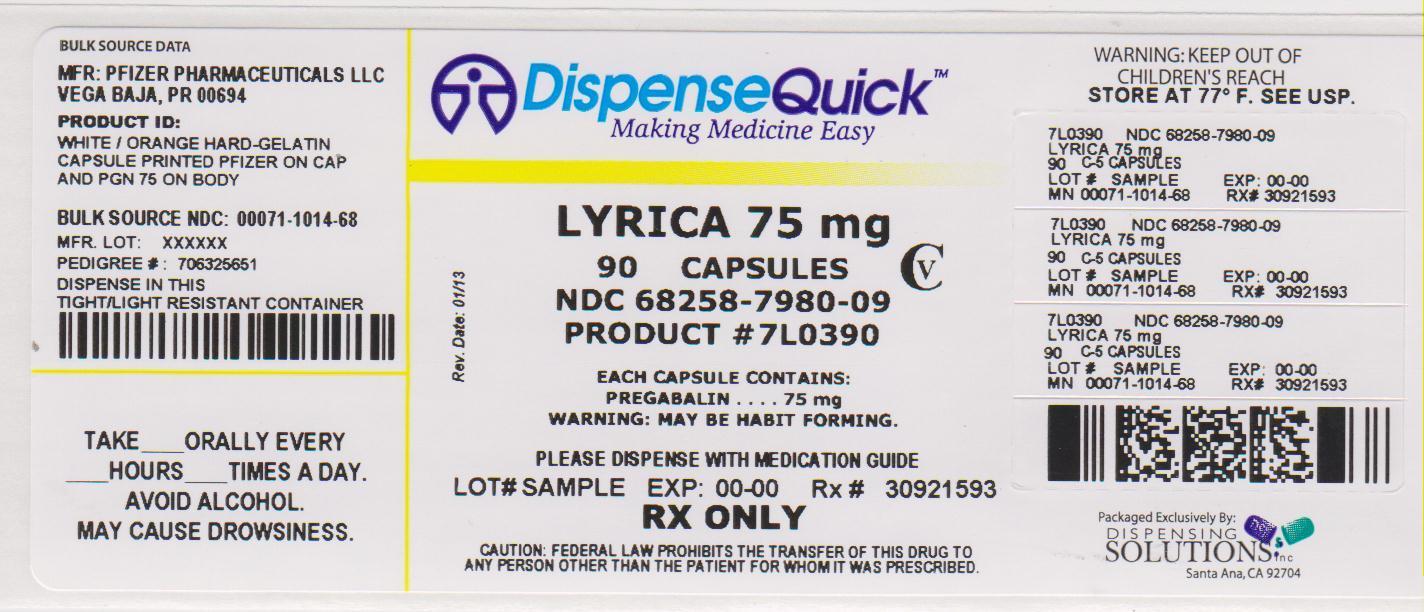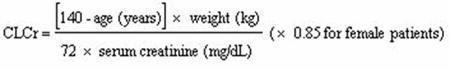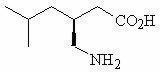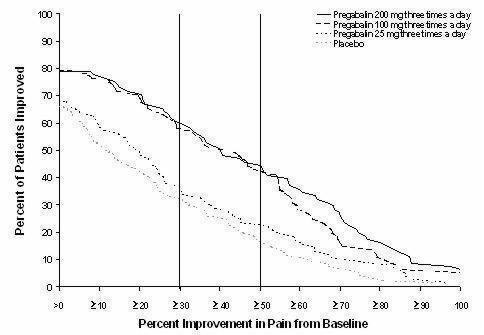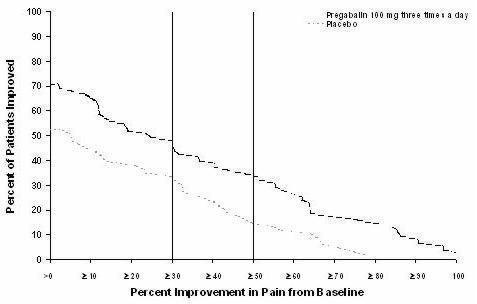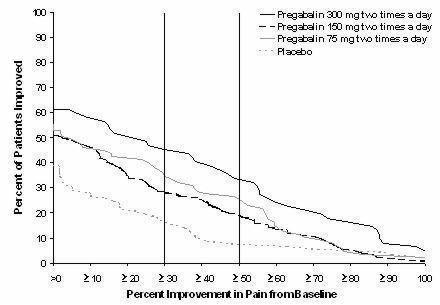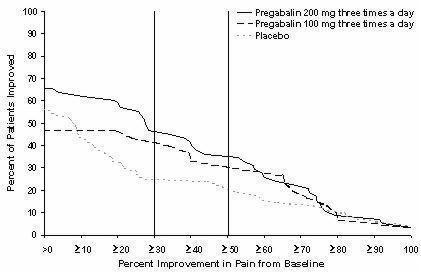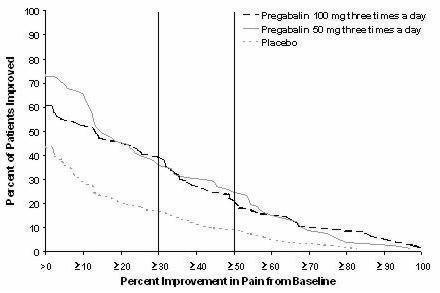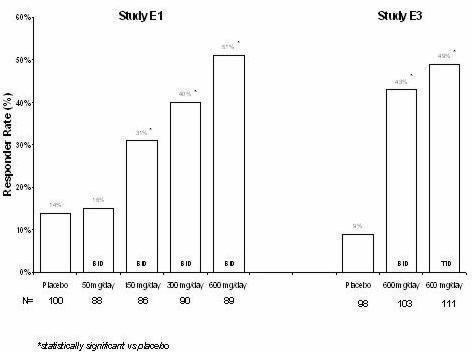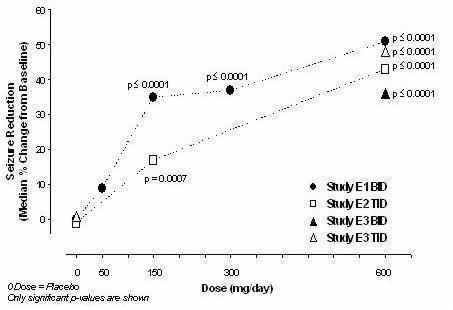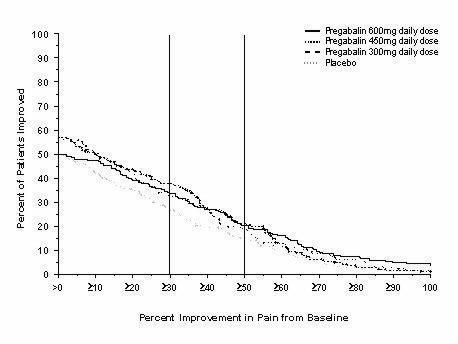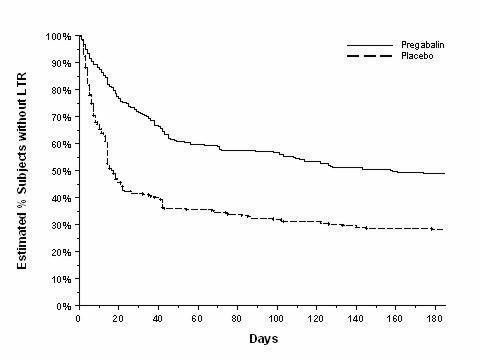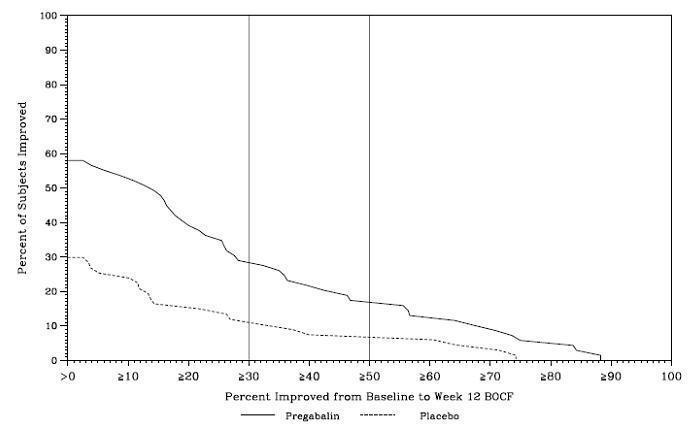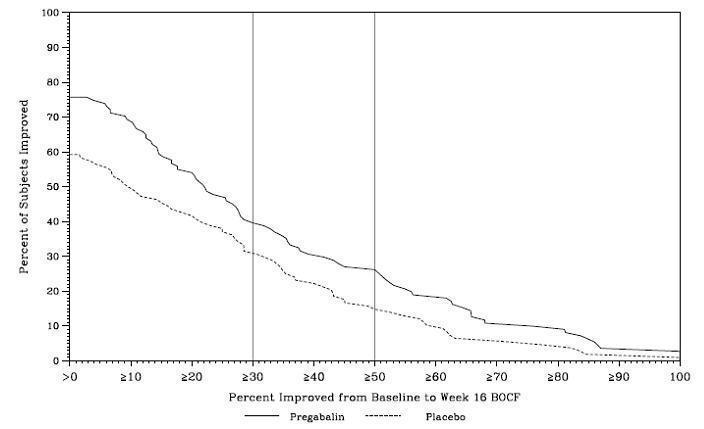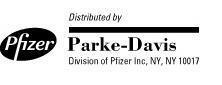 DRUG LABEL: Lyrica
NDC: 68258-7980 | Form: CAPSULE
Manufacturer: Dispensing Solutions, Inc.
Category: prescription | Type: HUMAN PRESCRIPTION DRUG LABEL
Date: 20130729
DEA Schedule: CV

ACTIVE INGREDIENTS: PREGABALIN 75 mg/1 1
INACTIVE INGREDIENTS: LACTOSE MONOHYDRATE; STARCH, CORN; TALC; GELATIN; TITANIUM DIOXIDE; SODIUM LAURYL SULFATE; SILICON DIOXIDE; FERRIC OXIDE RED; SHELLAC; FERROSOFERRIC OXIDE; PROPYLENE GLYCOL; POTASSIUM HYDROXIDE

HIGHLIGHTS OF PRESCRIBING INFORMATION

These highlights do not include all the information needed to use LYRICA safely and effectively. See full prescribing information for LYRICA.
LYRICA (pregabalin) Capsules, CV
LYRICA (pregabalin) Oral Solution, CV
Initial U.S. Approval: 2004

RECENT MAJOR CHANGES

Indications and Usage (1) | 6/2012
Dosage and Administration (2.5) | 6/2012
Warnings and Precautions (5.6) | 6/2012
Warnings and Precautions (5.8) | 6/2012

1 INDICATIONS AND USAGE

LYRICA is indicated for:

- Neuropathic pain associated with diabetic peripheral neuropathy (DPN) (1)
- Postherpetic neuralgia (PHN) (1)
- Adjunctive therapy for adult patients with partial onset seizures (1)
- Fibromyalgia (1)
- Neuropathic pain associated with spinal cord injury (1)

2 DOSAGE AND ADMINISTRATION

- For all indications, begin dosing at 150 mg/day. (2.1, 2.2, 2.3, 2.4, 2.5)
- Dosing recommendations:

INDICATION | Dosing Regimen | Maximum Dose
DPN Pain (2.1) | 3 divided doses per day | 300 mg/day within 1 week
PHN (2.2) | 2 or 3 divided doses per day | 300 mg/day within 1 week. Maximum dose of 600 mg/day.
Adjunctive Therapy for Adult Patients with Partial Onset Seizures (2.3) | 2 or 3 divided doses per day | Maximum dose of 600 mg/day.
Fibromyalgia (2.4) | 2 divided doses per day | 300 mg/day within 1 week. Maximum dose of 450 mg/day.
Neuropathic Pain Associated with Spinal Cord Injury (2.5) | 2 divided doses per day | 300 mg/day within 1 week. Maximum dose of 600 mg/day.

- Dose should be adjusted in patients with reduced renal function. (2.6)
- Oral Solution Concentration and Dispensing (2.7)

3 DOSAGE FORMS AND STRENGTHS

- Capsules: 25mg, 50 mg, 75 mg, 100 mg, 150 mg, 200 mg, 225 mg, and 300 mg. (3)
- Oral Solution: 20 mg/ mL. (3)

4 CONTRAINDICATIONS

- Known hypersensitivity to pregabalin or any of its components. (4)

5 WARNINGS AND PRECAUTIONS

- Angioedema (e.g. swelling of the throat, head and neck) can occur, and may be associated with life-threatening respiratory compromise requiring emergency treatment. Discontinue LYRICA immediately in these cases. (5.1)
- Hypersensitivity reactions (e.g. hives, dyspnea, and wheezing) can occur. Discontinue LYRICA immediately in these patients. (5.2)
- Increased seizure frequency may occur in patients with seizure disorders if LYRICA is rapidly discontinued. Withdraw LYRICA gradually over a minimum of 1 week. (5.3)
- Antiepileptic drugs, including LYRICA, increase the risk of suicidal thoughts or behavior. (5.4)
- LYRICA may cause peripheral edema. Exercise caution when co-administering LYRICA and thiazolidinedione antidiabetic agents. (5.5)
- LYRICA may cause dizziness and somnolence and impair patients' ability to drive or operate machinery.(5.6)

6 ADVERSE REACTIONS

Most common adverse reactions (≥ 5% and twice placebo) are dizziness, somnolence, dry mouth, edema, blurred vision, weight gain and thinking abnormal (primarily difficulty with concentration/attention). (6.1)

To report SUSPECTED ADVERSE REACTIONS, contact Pfizer at (800) 438-1985 or FDA at 1-800-FDA-1088 or www.fda.gov/medwatch

8 USE IN SPECIFIC POPULATIONS

- To enroll in the North American Antiepileptic Drug Pregnancy Registry call 1-888-233-2334 (toll free). (8.1)

FULL PRESCRIBING INFORMATION

1 INDICATIONS AND USAGE

LYRICA is indicated for:

- Management of neuropathic pain associated with diabetic peripheral neuropathy
- Management of postherpetic neuralgia
- Adjunctive therapy for adult patients with partial onset seizures
- Management of fibromyalgia
- Management of neuropathic pain associated with spinal cord injury

2 DOSAGE AND ADMINISTRATION

LYRICA is given orally with or without food.

When discontinuing LYRICA, taper gradually over a minimum of 1 week.

2.1 Neuropathic Pain Associated with Diabetic Peripheral Neuropathy

The maximum recommended dose of LYRICA is 100 mg three times a day (300 mg/day) in patients with creatinine clearance of at least 60 mL/min. Begin dosing at 50 mg three times a day (150 mg/day). The dose may be increased to 300 mg/day within 1 week based on efficacy and tolerability. Because LYRICA is eliminated primarily by renal excretion, adjust the dose in patients with reduced renal function [see Dosage and Administration (2.6)].

Although LYRICA was also studied at 600 mg/day, there is no evidence that this dose confers additional significant benefit and this dose was less well tolerated. In view of the dose-dependent adverse reactions, treatment with doses above 300 mg/day is not recommended [see Adverse Reactions (6.1)].

2.2 Postherpetic Neuralgia

The recommended dose of LYRICA is 75 to 150 mg two times a day, or 50 to 100 mg three times a day (150 to 300 mg/day) in patients with creatinine clearance of at least 60 mL/min. Begin dosing at 75 mg two times a day, or 50 mg three times a day (150 mg/day). The dose may be increased to 300 mg/day within 1 week based on efficacy and tolerability. Because LYRICA is eliminated primarily by renal excretion, adjust the dose in patients with reduced renal function [see Dosage and Administration (2.6)].

Patients who do not experience sufficient pain relief following 2 to 4 weeks of treatment with 300 mg/day, and who are able to tolerate LYRICA, may be treated with up to 300 mg two times a day, or 200 mg three times a day (600 mg/day). In view of the dose-dependent adverse reactions and the higher rate of treatment discontinuation due to adverse reactions, reserve dosing above 300 mg/day for those patients who have on-going pain and are tolerating 300 mg daily [see Adverse Reactions (6.1)].

2.3 Adjunctive Therapy for Adult Patients with Partial Onset Seizures

LYRICA at doses of 150 to 600 mg/day has been shown to be effective as adjunctive therapy in the treatment of partial onset seizures in adults. Both the efficacy and adverse event profiles of LYRICA have been shown to be dose-related. Administer the total daily dose in two or three divided doses. In general, it is recommended that patients be started on a total daily dose no greater than 150 mg/day (75 mg two times a day, or 50 mg three times a day). Based on individual patient response and tolerability, the dose may be increased to a maximum dose of 600 mg/day.

Because LYRICA is eliminated primarily by renal excretion, adjust the dose in patients with reduced renal function [see Dosage and Administration (2.6)].

The effect of dose escalation rate on the tolerability of LYRICA has not been formally studied.

The efficacy of add-on LYRICA in patients taking gabapentin has not been evaluated in controlled trials. Consequently, dosing recommendations for the use of LYRICA with gabapentin cannot be offered.

2.4 Management of Fibromyalgia

The recommended dose of LYRICA for fibromyalgia is 300 to 450 mg/day. Begin dosing at 75 mg two times a day (150 mg/day). The dose may be increased to 150 mg two times a day (300 mg/day) within 1 week based on efficacy and tolerability. Patients who do not experience sufficient benefit with 300 mg/day may be further increased to 225 mg two times a day (450 mg/day). Although LYRICA was also studied at 600 mg/day, there is no evidence that this dose confers additional benefit and this dose was less well tolerated. In view of the dose-dependent adverse reactions, treatment with doses above 450 mg/day is not recommended [see Adverse Reactions (6.1)]. Because LYRICA is eliminated primarily by renal excretion, adjust the dose in patients with reduced renal function [see Dosage and Administration (2.6)].

2.5 Neuropathic Pain Associated with Spinal Cord Injury

The recommended dose range of LYRICA for the treatment of neuropathic pain associated with spinal cord injury is 150 to 600 mg/day. The recommended starting dose is 75 mg two times a day (150 mg/day). The dose may be increased to 150 mg two times a day (300 mg/day) within 1 week based on efficacy and tolerability. Patients who do not experience sufficient pain relief after 2 to 3 weeks of treatment with 150 mg two times a day and who tolerate LYRICA may be treated with up to 300 mg two times a day [see Clinical Studies (14.5)]. Because LYRICA is eliminated primarily by renal excretion, adjust the dose in patients with reduced renal function [see Dosage and Administration (2.6)].

2.6 Patients with Renal Impairment

In view of dose-dependent adverse reactions and since LYRICA is eliminated primarily by renal excretion, adjust the dose in patients with reduced renal function. Base the dose adjustment in patients with renal impairment on creatinine clearance (CLcr), as indicated in Table 1. To use this dosing table, an estimate of the patient's CLcr in mL/min is needed. CLcr in mL/min may be estimated from serum creatinine (mg/dL) determination using the Cockcroft and Gault equation:

Next, refer to the Dosage and Administration section to determine the recommended total daily dose based on indication, for a patient with normal renal function (CLcr ≥60 mL/min). Then refer to Table 1 to determine the corresponding renal adjusted dose.

(For example: A patient initiating LYRICA therapy for postherpetic neuralgia with normal renal function (CLcr ≥60 mL/min), receives a total daily dose of 150 mg/day pregabalin. Therefore, a renal impaired patient with a CLcr of 50 mL/min would receive a total daily dose of 75 mg/day pregabalin administered in two or three divided doses.)

For patients undergoing hemodialysis, adjust the pregabalin daily dose based on renal function. In addition to the daily dose adjustment, administer a supplemental dose immediately following every 4-hour hemodialysis treatment (see Table 1).

Table 1. Pregabalin Dosage Adjustment Based on Renal Function
Creatinine Clearance (CLcr) (mL/min) | Total Pregabalin Daily Dose (mg/day) [Total daily dose (mg/day) should be divided as indicated by dose regimen to provide mg/dose.] |  |  |  | Dose Regimen
≥60 | 150 | 300 | 450 | 600 | BID or TID
30–60 | 75 | 150 | 225 | 300 | BID or TID
15–30 | 25–50 | 75 | 100–150 | 150 | QD or BID
<15 | 25 | 25–50 | 50–75 | 75 | QD
Supplementary dosage following hemodialysis (mg) [Supplementary dose is a single additional dose.]
Patients on the 25 mg QD regimen: take one supplemental dose of 25 mg or 50 mg
Patients on the 25–50 mg QD regimen: take one supplemental dose of 50 mg or 75 mg
Patients on the 50–75 mg QD regimen: take one supplemental dose of 75 mg or 100 mg
Patients on the 75 mg QD regimen: take one supplemental dose of 100 mg or 150 mg
TID= Three divided doses; BID = Two divided doses; QD = Single daily dose.

2.7 Oral Solution Concentration and Dispensing

The oral solution is 20 mg pregabalin per milliliter (mL) and prescriptions should be written in milligrams (mg). The pharmacist will calculate the applicable dose in mL for dispensing (e.g., 150 mg equals 7.5 mL oral solution).

3 DOSAGE FORMS AND STRENGTHS

Capsules: 25 mg, 50 mg, 75 mg, 100 mg, 150 mg, 200 mg, 225 mg, and 300 mg

Oral Solution: 20 mg/mL

[see Description (11) and How Supplied/Storage and Handling (16)].

4 CONTRAINDICATIONS

LYRICA is contraindicated in patients with known hypersensitivity to pregabalin or any of its components. Angioedema and hypersensitivity reactions have occurred in patients receiving pregabalin therapy.

5 WARNINGS AND PRECAUTIONS

5.1 Angioedema

There have been postmarketing reports of angioedema in patients during initial and chronic treatment with LYRICA. Specific symptoms included swelling of the face, mouth (tongue, lips, and gums), and neck (throat and larynx). There were reports of life-threatening angioedema with respiratory compromise requiring emergency treatment. Discontinue LYRICA immediately in patients with these symptoms.

Exercise caution when prescribing LYRICA to patients who have had a previous episode of angioedema. In addition, patients who are taking other drugs associated with angioedema (e.g., angiotensin converting enzyme inhibitors [ACE-inhibitors]) may be at increased risk of developing angioedema.

5.2 Hypersensitivity

There have been postmarketing reports of hypersensitivity in patients shortly after initiation of treatment with LYRICA. Adverse reactions included skin redness, blisters, hives, rash, dyspnea, and wheezing. Discontinue LYRICA immediately in patients with these symptoms.

5.3 Withdrawal of Antiepileptic Drugs (AEDs)

As with all AEDs, withdraw LYRICA gradually to minimize the potential of increased seizure frequency in patients with seizure disorders. If LYRICA is discontinued, taper the drug gradually over a minimum of 1 week.

5.4 Suicidal Behavior and Ideation

Antiepileptic drugs (AEDs), including LYRICA, increase the risk of suicidal thoughts or behavior in patients taking these drugs for any indication. Monitor patients treated with any AED for any indication for the emergence or worsening of depression, suicidal thoughts or behavior, and/or any unusual changes in mood or behavior.

Pooled analyses of 199 placebo-controlled clinical trials (mono- and adjunctive therapy) of 11 different AEDs showed that patients randomized to one of the AEDs had approximately twice the risk (adjusted Relative Risk 1.8, 95% CI:1.2, 2.7) of suicidal thinking or behavior compared to patients randomized to placebo. In these trials, which had a median treatment duration of 12 weeks, the estimated incidence rate of suicidal behavior or ideation among 27,863 AED-treated patients was 0.43%, compared to 0.24% among 16,029 placebo-treated patients, representing an increase of approximately one case of suicidal thinking or behavior for every 530 patients treated. There were four suicides in drug-treated patients in the trials and none in placebo-treated patients, but the number is too small to allow any conclusion about drug effect on suicide.

The increased risk of suicidal thoughts or behavior with AEDs was observed as early as one week after starting drug treatment with AEDs and persisted for the duration of treatment assessed. Because most trials included in the analysis did not extend beyond 24 weeks, the risk of suicidal thoughts or behavior beyond 24 weeks could not be assessed.

The risk of suicidal thoughts or behavior was generally consistent among drugs in the data analyzed. The finding of increased risk with AEDs of varying mechanisms of action and across a range of indications suggests that the risk applies to all AEDs used for any indication. The risk did not vary substantially by age (5–100 years) in the clinical trials analyzed.

Table 2 shows absolute and relative risk by indication for all evaluated AEDs.

Table 2. Risk by indication for antiepileptic drugs in the pooled analysis
Indication | Placebo Patients with Events Per 1000 Patients | Drug Patients with Events Per 1000 Patients | Relative Risk: Incidence of Events in Drug Patients/Incidence in Placebo Patients | Risk Difference: Additional Drug Patients with Events Per 1000 Patients
Epilepsy | 1.0 | 3.4 | 3.5 | 2.4
Psychiatric | 5.7 | 8.5 | 1.5 | 2.9
Other | 1.0 | 1.8 | 1.9 | 0.9
Total | 2.4 | 4.3 | 1.8 | 1.9

The relative risk for suicidal thoughts or behavior was higher in clinical trials for epilepsy than in clinical trials for psychiatric or other conditions, but the absolute risk differences were similar for the epilepsy and psychiatric indications.

Anyone considering prescribing LYRICA or any other AED must balance the risk of suicidal thoughts or behavior with the risk of untreated illness. Epilepsy and many other illnesses for which AEDs are prescribed are themselves associated with morbidity and mortality and an increased risk of suicidal thoughts and behavior. Should suicidal thoughts and behavior emerge during treatment, the prescriber needs to consider whether the emergence of these symptoms in any given patient may be related to the illness being treated.

Inform patients, their caregivers, and families that LYRICA and other AEDs increase the risk of suicidal thoughts and behavior and advise them of the need to be alert for the emergence or worsening of the signs and symptoms of depression, any unusual changes in mood or behavior, or the emergence of suicidal thoughts, behavior, or thoughts about self-harm. Report behaviors of concern immediately to healthcare providers.

5.5 Peripheral Edema

LYRICA treatment may cause peripheral edema. In short-term trials of patients without clinically significant heart or peripheral vascular disease, there was no apparent association between peripheral edema and cardiovascular complications such as hypertension or congestive heart failure. Peripheral edema was not associated with laboratory changes suggestive of deterioration in renal or hepatic function.

In controlled clinical trials the incidence of peripheral edema was 6% in the LYRICA group compared with 2% in the placebo group. In controlled clinical trials, 0.5% of LYRICA patients and 0.2% placebo patients withdrew due to peripheral edema.

Higher frequencies of weight gain and peripheral edema were observed in patients taking both LYRICA and a thiazolidinedione antidiabetic agent compared to patients taking either drug alone. The majority of patients using thiazolidinedione antidiabetic agents in the overall safety database were participants in studies of pain associated with diabetic peripheral neuropathy. In this population, peripheral edema was reported in 3% (2/60) of patients who were using thiazolidinedione antidiabetic agents only, 8% (69/859) of patients who were treated with LYRICA only, and 19% (23/120) of patients who were on both LYRICA and thiazolidinedione antidiabetic agents. Similarly, weight gain was reported in 0% (0/60) of patients on thiazolidinediones only; 4% (35/859) of patients on LYRICA only; and 7.5% (9/120) of patients on both drugs.

As the thiazolidinedione class of antidiabetic drugs can cause weight gain and/or fluid retention, possibly exacerbating or leading to heart failure, exercise caution when co-administering LYRICA and these agents.

Because there are limited data on congestive heart failure patients with New York Heart Association (NYHA) Class III or IV cardiac status, exercise caution when using LYRICA in these patients.

5.6 Dizziness and Somnolence

LYRICA may cause dizziness and somnolence. Inform patients that LYRICA-related dizziness and somnolence may impair their ability to perform tasks such as driving or operating machinery [see Patient Counseling Information (17.5)].

In the LYRICA controlled trials, dizziness was experienced by 30% of LYRICA-treated patients compared to 8% of placebo-treated patients; somnolence was experienced by 23% of LYRICA-treated patients compared to 8% of placebo-treated patients. Dizziness and somnolence generally began shortly after the initiation of LYRICA therapy and occurred more frequently at higher doses. Dizziness and somnolence were the adverse reactions most frequently leading to withdrawal (4% each) from controlled studies. In LYRICA-treated patients reporting these adverse reactions in short-term, controlled studies, dizziness persisted until the last dose in 30% and somnolence persisted until the last dose in 42% of patients [see Drug Interactions (7)].

5.7 Weight Gain

LYRICA treatment may cause weight gain. In LYRICA controlled clinical trials of up to 14 weeks, a gain of 7% or more over baseline weight was observed in 9% of LYRICA-treated patients and 2% of placebo-treated patients. Few patients treated with LYRICA (0.3%) withdrew from controlled trials due to weight gain. LYRICA associated weight gain was related to dose and duration of exposure, but did not appear to be associated with baseline BMI, gender, or age. Weight gain was not limited to patients with edema [see Warnings and Precautions (5.5)].

Although weight gain was not associated with clinically important changes in blood pressure in short-term controlled studies, the long-term cardiovascular effects of LYRICA-associated weight gain are unknown.

Among diabetic patients, LYRICA-treated patients gained an average of 1.6 kg (range: -16 to 16 kg), compared to an average 0.3 kg (range: -10 to 9 kg) weight gain in placebo patients. In a cohort of 333 diabetic patients who received LYRICA for at least 2 years, the average weight gain was 5.2 kg.

While the effects of LYRICA-associated weight gain on glycemic control have not been systematically assessed, in controlled and longer-term open label clinical trials with diabetic patients, LYRICA treatment did not appear to be associated with loss of glycemic control (as measured by HbA1C).

5.8 Abrupt or Rapid Discontinuation

Following abrupt or rapid discontinuation of LYRICA, some patients reported symptoms including insomnia, nausea, headache, anxiety, hyperhidrosis, and diarrhea. Taper LYRICA gradually over a minimum of 1 week rather than discontinuing the drug abruptly.

5.9 Tumorigenic Potential

In standard preclinical in vivo lifetime carcinogenicity studies of LYRICA, an unexpectedly high incidence of hemangiosarcoma was identified in two different strains of mice [see Nonclinical Toxicology (13.1)]. The clinical significance of this finding is unknown. Clinical experience during LYRICA's premarketing development provides no direct means to assess its potential for inducing tumors in humans.

In clinical studies across various patient populations, comprising 6396 patient-years of exposure in patients >12 years of age, new or worsening-preexisting tumors were reported in 57 patients. Without knowledge of the background incidence and recurrence in similar populations not treated with LYRICA, it is impossible to know whether the incidence seen in these cohorts is or is not affected by treatment.

5.10 Ophthalmological Effects

In controlled studies, a higher proportion of patients treated with LYRICA reported blurred vision (7%) than did patients treated with placebo (2%), which resolved in a majority of cases with continued dosing. Less than 1% of patients discontinued LYRICA treatment due to vision-related events (primarily blurred vision).

Prospectively planned ophthalmologic testing, including visual acuity testing, formal visual field testing and dilated funduscopic examination, was performed in over 3600 patients. In these patients, visual acuity was reduced in 7% of patients treated with LYRICA, and 5% of placebo-treated patients. Visual field changes were detected in 13% of LYRICA-treated, and 12% of placebo-treated patients. Funduscopic changes were observed in 2% of LYRICA-treated and 2% of placebo-treated patients.

Although the clinical significance of the ophthalmologic findings is unknown, inform patients to notify their physician if changes in vision occur. If visual disturbance persists, consider further assessment. Consider more frequent assessment for patients who are already routinely monitored for ocular conditions [see Patient Counseling Information (17.8)].

5.11 Creatine Kinase Elevations

LYRICA treatment was associated with creatine kinase elevations. Mean changes in creatine kinase from baseline to the maximum value were 60 U/L for LYRICA-treated patients and 28 U/L for the placebo patients. In all controlled trials across multiple patient populations, 1.5% of patients on LYRICA and 0.7% of placebo patients had a value of creatine kinase at least three times the upper limit of normal. Three LYRICA treated subjects had events reported as rhabdomyolysis in premarketing clinical trials. The relationship between these myopathy events and LYRICA is not completely understood because the cases had documented factors that may have caused or contributed to these events. Instruct patients to promptly report unexplained muscle pain, tenderness, or weakness, particularly if these muscle symptoms are accompanied by malaise or fever. Discontinue treatment with LYRICA if myopathy is diagnosed or suspected or if markedly elevated creatine kinase levels occur.

5.12 Decreased Platelet Count

LYRICA treatment was associated with a decrease in platelet count. LYRICA-treated subjects experienced a mean maximal decrease in platelet count of 20 × 10^3/µL, compared to 11 × 10^3/µL in placebo patients. In the overall database of controlled trials, 2% of placebo patients and 3% of LYRICA patients experienced a potentially clinically significant decrease in platelets, defined as 20% below baseline value and <150 × 10^3/µL. A single LYRICA treated subject developed severe thrombocytopenia with a platelet count less than 20 × 10^3/ µL. In randomized controlled trials, LYRICA was not associated with an increase in bleeding-related adverse reactions.

5.13 PR Interval Prolongation

LYRICA treatment was associated with PR interval prolongation. In analyses of clinical trial ECG data, the mean PR interval increase was 3–6 msec at LYRICA doses ≥300 mg/day. This mean change difference was not associated with an increased risk of PR increase ≥25% from baseline, an increased percentage of subjects with on-treatment PR >200 msec, or an increased risk of adverse reactions of second or third degree AV block.

Subgroup analyses did not identify an increased risk of PR prolongation in patients with baseline PR prolongation or in patients taking other PR prolonging medications. However, these analyses cannot be considered definitive because of the limited number of patients in these categories.

6 ADVERSE REACTIONS

6.1 Clinical Trials Experience

Because clinical trials are conducted under widely varying conditions, adverse reaction rates observed in the clinical trials of a drug cannot be directly compared to rates in the clinical trials of another drug and may not reflect the rates observed in practice.

In all controlled and uncontrolled trials across various patient populations during the premarketing development of LYRICA, more than 10,000 patients have received LYRICA. Approximately 5000 patients were treated for 6 months or more, over 3100 patients were treated for 1 year or longer, and over 1400 patients were treated for at least 2 years.

Adverse Reactions Most Commonly Leading to Discontinuation in All Premarketing Controlled Clinical Studies

In premarketing controlled trials of all populations combined, 14% of patients treated with LYRICA and 7% of patients treated with placebo discontinued prematurely due to adverse reactions. In the LYRICA treatment group, the adverse reactions most frequently leading to discontinuation were dizziness (4%) and somnolence (4%). In the placebo group, 1% of patients withdrew due to dizziness and <1% withdrew due to somnolence. Other adverse reactions that led to discontinuation from controlled trials more frequently in the LYRICA group compared to the placebo group were ataxia, confusion, asthenia, thinking abnormal, blurred vision, incoordination, and peripheral edema (1% each).

Most Common Adverse Reactions in All Premarketing Controlled Clinical Studies

In premarketing controlled trials of all patient populations combined, dizziness, somnolence, dry mouth, edema, blurred vision, weight gain, and "thinking abnormal" (primarily difficulty with concentration/attention) were more commonly reported by subjects treated with LYRICA than by subjects treated with placebo (≥5% and twice the rate of that seen in placebo).

Controlled Studies with Neuropathic Pain Associated with Diabetic Peripheral Neuropathy

Adverse Reactions Leading to Discontinuation

In clinical trials in patients with neuropathic pain associated with diabetic peripheral neuropathy, 9% of patients treated with LYRICA and 4% of patients treated with placebo discontinued prematurely due to adverse reactions. In the LYRICA treatment group, the most common reasons for discontinuation due to adverse reactions were dizziness (3%) and somnolence (2%). In comparison, <1% of placebo patients withdrew due to dizziness and somnolence. Other reasons for discontinuation from the trials, occurring with greater frequency in the LYRICA group than in the placebo group, were asthenia, confusion, and peripheral edema. Each of these events led to withdrawal in approximately 1% of patients.

Most Common Adverse Reactions

Table 3 lists all adverse reactions, regardless of causality, occurring in ≥1% of patients with neuropathic pain associated with diabetic neuropathy in the combined LYRICA group for which the incidence was greater in this combined LYRICA group than in the placebo group. A majority of pregabalin-treated patients in clinical studies had adverse reactions with a maximum intensity of "mild" or "moderate".

Table 3. Treatment-emergent adverse reaction incidence in controlled trials in neuropathic pain associated with diabetic peripheral neuropathy (events in at least 1% of all LYRICA-treated patients and at least numerically more in all LYRICA than in the placebo group)
Body system Preferred term | 75 mg/day | 150 mg/day | 300 mg/day | 600 mg/day | All PGB [PGB: pregabalin] | Placebo
 | [N=77] % | [N=212] % | [N=321] % | [N=369] % | [N=979] % | [N=459] %
Body as a whole
Asthenia | 4 | 2 | 4 | 7 | 5 | 2
Accidental injury | 5 | 2 | 2 | 6 | 4 | 3
Back pain | 0 | 2 | 1 | 2 | 2 | 0
Chest pain | 4 | 1 | 1 | 2 | 2 | 1
Face edema | 0 | 1 | 1 | 2 | 1 | 0
Digestive system
Dry mouth | 3 | 2 | 5 | 7 | 5 | 1
Constipation | 0 | 2 | 4 | 6 | 4 | 2
Flatulence | 3 | 0 | 2 | 3 | 2 | 1
Metabolic and
nutritional disorders
Peripheral edema | 4 | 6 | 9 | 12 | 9 | 2
Weight gain | 0 | 4 | 4 | 6 | 4 | 0
Edema | 0 | 2 | 4 | 2 | 2 | 0
Hypoglycemia | 1 | 3 | 2 | 1 | 2 | 1
Nervous system
Dizziness | 8 | 9 | 23 | 29 | 21 | 5
Somnolence | 4 | 6 | 13 | 16 | 12 | 3
Neuropathy | 9 | 2 | 2 | 5 | 4 | 3
Ataxia | 6 | 1 | 2 | 4 | 3 | 1
Vertigo | 1 | 2 | 2 | 4 | 3 | 1
Confusion | 0 | 1 | 2 | 3 | 2 | 1
Euphoria | 0 | 0 | 3 | 2 | 2 | 0
Incoordination | 1 | 0 | 2 | 2 | 2 | 0
Thinking abnormal [Thinking abnormal primarily consists of events related to difficulty with concentration/attention but also includes events related to cognition and language problems and slowed thinking.] | 1 | 0 | 1 | 3 | 2 | 0
Tremor | 1 | 1 | 1 | 2 | 1 | 0
Abnormal gait | 1 | 0 | 1 | 3 | 1 | 0
Amnesia | 3 | 1 | 0 | 2 | 1 | 0
Nervousness | 0 | 1 | 1 | 1 | 1 | 0
Respiratory system
Dyspnea | 3 | 0 | 2 | 2 | 2 | 1
Special senses
Blurry vision [Investigator term; summary level term is amblyopia] | 3 | 1 | 3 | 6 | 4 | 2
Abnormal vision | 1 | 0 | 1 | 1 | 1 | 0

Controlled Studies in Postherpetic Neuralgia

Adverse Reactions Leading to Discontinuation

In clinical trials in patients with postherpetic neuralgia, 14% of patients treated with LYRICA and 7% of patients treated with placebo discontinued prematurely due to adverse reactions. In the LYRICA treatment group, the most common reasons for discontinuation due to adverse reactions were dizziness (4%) and somnolence (3%). In comparison, less than 1% of placebo patients withdrew due to dizziness and somnolence. Other reasons for discontinuation from the trials, occurring in greater frequency in the LYRICA group than in the placebo group, were confusion (2%), as well as peripheral edema, asthenia, ataxia, and abnormal gait (1% each).

Most Common Adverse Reactions

Table 4 lists all adverse reactions, regardless of causality, occurring in ≥ 1% of patients with neuropathic pain associated with postherpetic neuralgia in the combined LYRICA group for which the incidence was greater in this combined LYRICA group than in the placebo group. In addition, an event is included, even if the incidence in the all LYRICA group is not greater than in the placebo group, if the incidence of the event in the 600 mg/day group is more than twice that in the placebo group. A majority of pregabalin-treated patients in clinical studies had adverse reactions with a maximum intensity of "mild" or "moderate". Overall, 12.4% of all pregabalin-treated patients and 9.0% of all placebo-treated patients had at least one severe event while 8% of pregabalin-treated patients and 4.3% of placebo-treated patients had at least one severe treatment-related adverse event.

Table 4. Treatment-emergent adverse reaction incidence in controlled trials in neuropathic pain associated with postherpetic neuralgia (events in at least 1% of all LYRICA-treated patients and at least numerically more in all LYRICA than in the placebo group)
Body system Preferred term | 75 mg/d | 150 mg/d | 300 mg/d | 600 mg/d | All PGB [PGB: pregabalin] | Placebo
 | [N=84] % | [N=302] % | [N=312] % | [N=154] % | [N=852] % | [N=398] %
Body as a whole
Infection | 14 | 8 | 6 | 3 | 7 | 4
Headache | 5 | 9 | 5 | 8 | 7 | 5
Pain | 5 | 4 | 5 | 5 | 5 | 4
Accidental injury | 4 | 3 | 3 | 5 | 3 | 2
Flu syndrome | 1 | 2 | 2 | 1 | 2 | 1
Face edema | 0 | 2 | 1 | 3 | 2 | 1
Digestive system
Dry mouth | 7 | 7 | 6 | 15 | 8 | 3
Constipation | 4 | 5 | 5 | 5 | 5 | 2
Flatulence | 2 | 1 | 2 | 3 | 2 | 1
Vomiting | 1 | 1 | 3 | 3 | 2 | 1
Metabolic and
nutritional disorders
Peripheral edema | 0 | 8 | 16 | 16 | 12 | 4
Weight gain | 1 | 2 | 5 | 7 | 4 | 0
Edema | 0 | 1 | 2 | 6 | 2 | 1
Musculoskeletal system
Myasthenia | 1 | 1 | 1 | 1 | 1 | 0
Nervous system
Dizziness | 11 | 18 | 31 | 37 | 26 | 9
Somnolence | 8 | 12 | 18 | 25 | 16 | 5
Ataxia | 1 | 2 | 5 | 9 | 5 | 1
Abnormal gait | 0 | 2 | 4 | 8 | 4 | 1
Confusion | 1 | 2 | 3 | 7 | 3 | 0
Thinking abnormal [Thinking abnormal primarily consists of events related to difficulty with concentration/attention but also includes events related to cognition and language problems and slowed thinking.] | 0 | 2 | 1 | 6 | 2 | 2
Incoordination | 2 | 2 | 1 | 3 | 2 | 0
Amnesia | 0 | 1 | 1 | 4 | 2 | 0
Speech disorder | 0 | 0 | 1 | 3 | 1 | 0
Respiratory system
Bronchitis | 0 | 1 | 1 | 3 | 1 | 1
Special senses
Blurry vision [Investigator term; summary level term is amblyopia] | 1 | 5 | 5 | 9 | 5 | 3
Diplopia | 0 | 2 | 2 | 4 | 2 | 0
Abnormal vision | 0 | 1 | 2 | 5 | 2 | 0
Eye Disorder | 0 | 1 | 1 | 2 | 1 | 0
Urogenital System
Urinary Incontinence | 0 | 1 | 1 | 2 | 1 | 0

Controlled Add-On Studies in Adjunctive Therapy for Adult Patients with Partial Onset Seizures

Adverse Reactions Leading to Discontinuation

Approximately 15% of patients receiving LYRICA and 6% of patients receiving placebo in add-on epilepsy trials discontinued prematurely due to adverse reactions. In the LYRICA treatment group, the adverse reactions most frequently leading to discontinuation were dizziness (6%), ataxia (4%), and somnolence (3%). In comparison, <1% of patients in the placebo group withdrew due to each of these events. Other adverse reactions that led to discontinuation of at least 1% of patients in the LYRICA group and at least twice as frequently compared to the placebo group were asthenia, diplopia, blurred vision, thinking abnormal, nausea, tremor, vertigo, headache, and confusion (which each led to withdrawal in 2% or less of patients).

Most Common Adverse Reactions

Table 5 lists all dose-related adverse reactions occurring in at least 2% of all LYRICA-treated patients. Dose-relatedness was defined as the incidence of the adverse event in the 600 mg/day group was at least 2% greater than the rate in both the placebo and 150 mg/day groups. In these studies, 758 patients received LYRICA and 294 patients received placebo for up to 12 weeks. Because patients were also treated with 1 to 3 other AEDs, it is not possible to determine whether the following adverse reactions can be ascribed to LYRICA alone, or the combination of LYRICA and other AEDs. A majority of pregabalin-treated patients in clinical studies had adverse reactions with a maximum intensity of "mild" or "moderate".

Table 5. Dose-related treatment-emergent adverse reaction incidence in controlled trials in adjunctive therapy for adult patients with partial onset seizures (events in at least 2% of all LYRICA-treated patients and the adverse reaction in the 600 mg/day group was ≥2% the rate in both the placebo and 150 mg/day groups)
Body System Preferred Term | 150 mg/d [N = 185] % | 300 mg/d [N = 90] % | 600 mg/d [N = 395] % | All PGB [PGB: pregabalin] [N = 670] [Excludes patients who received the 50 mg dose in Study E1.] % | Placebo [N = 294] %
Body as a Whole
Accidental Injury | 7 | 11 | 10 | 9 | 5
Pain | 3 | 2 | 5 | 4 | 3
Digestive System
Increased Appetite | 2 | 3 | 6 | 5 | 1
Dry Mouth | 1 | 2 | 6 | 4 | 1
Constipation | 1 | 1 | 7 | 4 | 2
Metabolic and Nutritional Disorders
Weight Gain | 5 | 7 | 16 | 12 | 1
Peripheral Edema | 3 | 3 | 6 | 5 | 2
Nervous System
Dizziness | 18 | 31 | 38 | 32 | 11
Somnolence | 11 | 18 | 28 | 22 | 11
Ataxia | 6 | 10 | 20 | 15 | 4
Tremor | 3 | 7 | 11 | 8 | 4
Thinking Abnormal [Thinking abnormal primarily consists of events related to difficulty with concentration/attention but also includes events related to cognition and language problems and slowed thinking.] | 4 | 8 | 9 | 8 | 2
Amnesia | 3 | 2 | 6 | 5 | 2
Speech Disorder | 1 | 2 | 7 | 5 | 1
Incoordination | 1 | 3 | 6 | 4 | 1
Abnormal Gait | 1 | 3 | 5 | 4 | 0
Twitching | 0 | 4 | 5 | 4 | 1
Confusion | 1 | 2 | 5 | 4 | 2
Myoclonus | 1 | 0 | 4 | 2 | 0
Special Senses
Blurred Vision [Investigator term; summary level term is amblyopia.] | 5 | 8 | 12 | 10 | 4
Diplopia | 5 | 7 | 12 | 9 | 4
Abnormal Vision | 3 | 1 | 5 | 4 | 1

Controlled Studies with Fibromyalgia

Adverse Reactions Leading to Discontinuation

In clinical trials of patients with fibromyalgia, 19% of patients treated with pregabalin (150–600 mg/day) and 10% of patients treated with placebo discontinued prematurely due to adverse reactions. In the pregabalin treatment group, the most common reasons for discontinuation due to adverse reactions were dizziness (6%) and somnolence (3%). In comparison, <1% of placebo-treated patients withdrew due to dizziness and somnolence. Other reasons for discontinuation from the trials, occurring with greater frequency in the pregabalin treatment group than in the placebo treatment group, were fatigue, headache, balance disorder, and weight increased. Each of these adverse reactions led to withdrawal in approximately 1% of patients.

Most Common Adverse Reactions

Table 6 lists all adverse reactions, regardless of causality, occurring in ≥2% of patients with fibromyalgia in the 'all pregabalin' treatment group for which the incidence was greater than in the placebo treatment group. A majority of pregabalin-treated patients in clinical studies experienced adverse reactions with a maximum intensity of "mild" or "moderate".

Table 6. Treatment-emergent adverse reaction incidence in controlled trials in fibromyalgia (events) in at least 2% of all LYRICA-treated patients and occurring more frequently in the all pregabalin-group than in the placebo treatment group)
System Organ Class Preferred term | 150 mg/d | 300 mg/d | 450 mg/d | 600 mg/d | All PGB [PGB: pregabalin] | Placebo
 | [N=132] % | [N=502] % | [N=505] % | [N=378] % | [N=1517] % | [N=505] %
Ear and Labyrinth
Disorders
Vertigo | 2 | 2 | 2 | 1 | 2 | 0
Eye Disorders
Vision blurred | 8 | 7 | 7 | 12 | 8 | 1
Gastrointestinal
Disorders
Dry mouth | 7 | 6 | 9 | 9 | 8 | 2
Constipation | 4 | 4 | 7 | 10 | 7 | 2
Vomiting | 2 | 3 | 3 | 2 | 3 | 2
Flatulence | 1 | 1 | 2 | 2 | 2 | 1
Abdominal distension | 2 | 2 | 2 | 2 | 2 | 1
General Disorders and
Administrative Site
Conditions
Fatigue | 5 | 7 | 6 | 8 | 7 | 4
Edema peripheral | 5 | 5 | 6 | 9 | 6 | 2
Chest pain | 2 | 1 | 1 | 2 | 2 | 1
Feeling abnormal | 1 | 3 | 2 | 2 | 2 | 0
Edema | 1 | 2 | 1 | 2 | 2 | 1
Feeling drunk | 1 | 2 | 1 | 2 | 2 | 0
Infections and
Infestations
Sinusitis | 4 | 5 | 7 | 5 | 5 | 4
Investigations
Weight increased | 8 | 10 | 10 | 14 | 11 | 2
Metabolism and
Nutrition Disorders
Increased appetite | 4 | 3 | 5 | 7 | 5 | 1
Fluid retention | 2 | 3 | 3 | 2 | 2 | 1
Musculoskeletal and
Connective Tissue
Disorders
Arthralgia | 4 | 3 | 3 | 6 | 4 | 2
Muscle spasms | 2 | 4 | 4 | 4 | 4 | 2
Back pain | 2 | 3 | 4 | 3 | 3 | 3
Nervous System
Disorders
Dizziness | 23 | 31 | 43 | 45 | 38 | 9
Somnolence | 13 | 18 | 22 | 22 | 20 | 4
Headache | 11 | 12 | 14 | 10 | 12 | 12
Disturbance in attention | 4 | 4 | 6 | 6 | 5 | 1
Balance disorder | 2 | 3 | 6 | 9 | 5 | 0
Memory impairment | 1 | 3 | 4 | 4 | 3 | 0
Coordination abnormal | 2 | 1 | 2 | 2 | 2 | 1
Hypoesthesia | 2 | 2 | 3 | 2 | 2 | 1
Lethargy | 2 | 2 | 1 | 2 | 2 | 0
Tremor | 0 | 1 | 3 | 2 | 2 | 0
Psychiatric Disorders
Euphoric Mood | 2 | 5 | 6 | 7 | 6 | 1
Confusional state | 0 | 2 | 3 | 4 | 3 | 0
Anxiety | 2 | 2 | 2 | 2 | 2 | 1
Disorientation | 1 | 0 | 2 | 1 | 2 | 0
Depression | 2 | 2 | 2 | 2 | 2 | 2
Respiratory, Thoracic
and Mediastinal Disorders
Pharyngolaryngeal pain | 2 | 1 | 3 | 3 | 2 | 2

Controlled Studies in Neuropathic Pain Associated with Spinal Cord Injury

Adverse Reactions Leading to Discontinuation

In clinical trials of patients with neuropathic pain associated with spinal cord injury, 13% of patients treated with pregabalin and 10% of patients treated with placebo discontinued prematurely due to adverse reactions. In the pregabalin treatment group, the most common reasons for discontinuation due to adverse reactions were somnolence (3%) and edema (2%). In comparison, none of the placebo-treated patients withdrew due to somnolence and edema. Other reasons for discontinuation from the trials, occurring with greater frequency in the pregabalin treatment group than in the placebo treatment group, were fatigue and balance disorder. Each of these adverse reactions led to withdrawal in less than 2% of patients.

Most Common Adverse Reactions

Table 7 lists all adverse reactions, regardless of causality, occurring in ≥2% of patients with neuropathic pain associated with spinal cord injury in the controlled trials. A majority of pregabalin-treated patients in clinical studies experienced adverse reactions with a maximum intensity of "mild" or "moderate".

Table 7. Treatment-emergent adverse reaction incidence in controlled trials in neuropathic pain associated with spinal cord injury (events in at least 2% of all LYRICA-treated patients and occurring more frequently in the all pregabalin-group than in the placebo treatment group)
System Organ Class Preferred term | PGB [PGB: Pregabalin] (N=182) | Placebo (N=174)
System Organ Class Preferred term | % | %
Ear and labryrinth disorders
Vertigo | 2.7 | 1.1
Eye disorders
Vision blurred | 6.6 | 1.1
Gastrointestinal disorders
Dry mouth | 11.0 | 2.9
Constipation | 8.2 | 5.7
Nausea | 4.9 | 4.0
Vomiting | 2.7 | 1.1
General disorders and
administration site conditions
Fatigue | 11.0 | 4.0
Edema peripheral | 10.4 | 5.2
Edema | 8.2 | 1.1
Pain | 3.3 | 1.1
Infections and infestations
Nasopharyngitis | 8.2 | 4.6
Investigations
Weight increased | 3.3 | 1.1
Blood creatine phosphokinase increased | 2.7 | 0
Musculoskeletal and
connective tissue disorders
Muscular weakness | 4.9 | 1.7
Pain in extremity | 3.3 | 2.3
Neck pain | 2.7 | 1.1
Back pain | 2.2 | 1.7
Joint swelling | 2.2 | 0
Nervous system disorders
Somnolence | 35.7 | 11.5
Dizziness | 20.9 | 6.9
Disturbance in attention | 3.8 | 0
Memory impairment | 3.3 | 1.1
Paresthesia | 2.2 | 0.6
Psychiatric disorders
Insomnia | 3.8 | 2.9
Euphoric mood | 2.2 | 0.6
Renal and urinary disorders
Urinary incontinence | 2.7 | 1.1
Skin and subcutaneous tissue disorders
Decubitus ulcer | 2.7 | 1.1
Vascular disorders
Hypertension | 2.2 | 1.1
Hypotension | 2.2 | 0

Other Adverse Reactions Observed During the Clinical Studies of LYRICA

Following is a list of treatment-emergent adverse reactions reported by patients treated with LYRICA during all clinical trials. The listing does not include those events already listed in the previous tables or elsewhere in labeling, those events for which a drug cause was remote, those events which were so general as to be uninformative, and those events reported only once which did not have a substantial probability of being acutely life-threatening.

Events are categorized by body system and listed in order of decreasing frequency according to the following definitions: frequent adverse reactions are those occurring on one or more occasions in at least 1/100 patients; infrequent adverse reactions are those occurring in 1/100 to 1/1000 patients; rare reactions are those occurring in fewer than 1/1000 patients. Events of major clinical importance are described in the Warnings and Precautions section (5).

Body as a Whole – Frequent: Abdominal pain, Allergic reaction, Fever, Infrequent: Abscess, Cellulitis, Chills, Malaise, Neck rigidity, Overdose, Pelvic pain, Photosensitivity reaction, Rare: Anaphylactoid reaction, Ascites, Granuloma, Hangover effect, Intentional Injury, Retroperitoneal Fibrosis, Shock

Cardiovascular System – Infrequent: Deep thrombophlebitis, Heart failure, Hypotension, Postural hypotension, Retinal vascular disorder, Syncope; Rare: ST Depressed, Ventricular Fibrillation

Digestive System – Frequent: Gastroenteritis, Increased appetite; Infrequent: Cholecystitis, Cholelithiasis, Colitis, Dysphagia, Esophagitis, Gastritis, Gastrointestinal hemorrhage, Melena, Mouth ulceration, Pancreatitis, Rectal hemorrhage, Tongue edema; Rare: Aphthous stomatitis, Esophageal Ulcer, Periodontal abscess

Hemic and Lymphatic System – Frequent: Ecchymosis; Infrequent: Anemia, Eosinophilia, Hypochromic anemia, Leukocytosis, Leukopenia, Lymphadenopathy, Thrombocytopenia; Rare: Myelofibrosis, Polycythemia, Prothrombin decreased, Purpura, Thrombocythemia

Metabolic and Nutritional Disorders – Rare: Glucose Tolerance Decreased, Urate Crystalluria

Musculoskeletal System – Frequent: Arthralgia, Leg cramps, Myalgia, Myasthenia; Infrequent: Arthrosis; Rare: Chondrodystrophy, Generalized Spasm

Nervous System – Frequent: Anxiety, Depersonalization, Hypertonia, Hypoesthesia, Libido decreased, Nystagmus, Paresthesia, Sedation, Stupor, Twitching; Infrequent: Abnormal dreams, Agitation, Apathy, Aphasia, Circumoral paresthesia, Dysarthria, Hallucinations, Hostility, Hyperalgesia, Hyperesthesia, Hyperkinesia, Hypokinesia, Hypotonia, Libido increased, Myoclonus, Neuralgia, Rare: Addiction, Cerebellar syndrome, Cogwheel rigidity, Coma, Delirium, Delusions, Dysautonomia, Dyskinesia, Dystonia, Encephalopathy, Extrapyramidal syndrome, Guillain-Barré syndrome, Hypalgesia, Intracranial hypertension, Manic reaction, Paranoid reaction, Peripheral neuritis, Personality disorder, Psychotic depression, Schizophrenic reaction, Sleep disorder, Torticollis, Trismus

Respiratory System – Rare: Apnea, Atelectasis, Bronchiolitis, Hiccup, Laryngismus, Lung edema, Lung fibrosis, Yawn

Skin and Appendages – Frequent: Pruritus, Infrequent: Alopecia, Dry skin, Eczema, Hirsutism, Skin ulcer, Urticaria, Vesiculobullous rash; Rare: Angioedema, Exfoliative dermatitis, Lichenoid dermatitis, Melanosis, Nail Disorder, Petechial rash, Purpuric rash, Pustular rash, Skin atrophy, Skin necrosis, Skin nodule, Stevens-Johnson syndrome, Subcutaneous nodule

Special senses – Frequent: Conjunctivitis, Diplopia, Otitis media, Tinnitus; Infrequent: Abnormality of accommodation, Blepharitis, Dry eyes, Eye hemorrhage, Hyperacusis, Photophobia, Retinal edema, Taste loss, Taste perversion; Rare: Anisocoria, Blindness, Corneal ulcer, Exophthalmos, Extraocular palsy, Iritis, Keratitis, Keratoconjunctivitis, Miosis, Mydriasis, Night blindness, Ophthalmoplegia, Optic atrophy, Papilledema, Parosmia, Ptosis, Uveitis

Urogenital System – Frequent: Anorgasmia, Impotence, Urinary frequency, Urinary incontinence; Infrequent: Abnormal ejaculation, Albuminuria, Amenorrhea, Dysmenorrhea, Dysuria, Hematuria, Kidney calculus, Leukorrhea, Menorrhagia, Metrorrhagia, Nephritis, Oliguria, Urinary retention, Urine abnormality; Rare: Acute kidney failure, Balanitis, Bladder Neoplasm, Cervicitis, Dyspareunia, Epididymitis, Female lactation, Glomerulitis, Ovarian disorder, Pyelonephritis

Comparison of Gender and Race

The overall adverse event profile of pregabalin was similar between women and men. There are insufficient data to support a statement regarding the distribution of adverse experience reports by race.

6.2 Post-marketing Experience

The following adverse reactions have been identified during postapproval use of LYRICA. Because these reactions are reported voluntarily from a population of uncertain size, it is not always possible to reliably estimate their frequency or establish a causal relationship to drug exposure.

Nervous System Disorders – Headache

Gastrointestinal Disorders – Nausea, Diarrhea

Reproductive System and Breast Disorders – Gynecomastia, Breast Enlargement

In addition, there are post-marketing reports of events related to reduced lower gastrointestinal tract function (e.g., intestinal obstruction, paralytic ileus, constipation) when LYRICA was co-administered with medications that have the potential to produce constipation, such as opioid analgesics. There are also post-marketing reports of respiratory failure and coma in patients taking pregabalin and other CNS depressant medications.

7 DRUG INTERACTIONS

Since LYRICA is predominantly excreted unchanged in the urine, undergoes negligible metabolism in humans (<2% of a dose recovered in urine as metabolites), and does not bind to plasma proteins, its pharmacokinetics are unlikely to be affected by other agents through metabolic interactions or protein binding displacement. In vitro and in vivo studies showed that LYRICA is unlikely to be involved in significant pharmacokinetic drug interactions. Specifically, there are no pharmacokinetic interactions between pregabalin and the following antiepileptic drugs: carbamazepine, valproic acid, lamotrigine, phenytoin, phenobarbital, and topiramate. Important pharmacokinetic interactions would also not be expected to occur between LYRICA and commonly used antiepileptic drugs [see Clinical Pharmacology (12)].

Pharmacodynamics

Multiple oral doses of LYRICA were co-administered with oxycodone, lorazepam, or ethanol. Although no pharmacokinetic interactions were seen, additive effects on cognitive and gross motor functioning were seen when LYRICA was co-administered with these drugs. No clinically important effects on respiration were seen.

8 USE IN SPECIFIC POPULATIONS

8.1 Pregnancy

TERATOGENIC EFFECTS

Pregnancy Category C. Increased incidences of fetal structural abnormalities and other manifestations of developmental toxicity, including lethality, growth retardation, and nervous and reproductive system functional impairment, were observed in the offspring of rats and rabbits given pregabalin during pregnancy, at doses that produced plasma pregabalin exposures (AUC) ≥5 times human exposure at the maximum recommended dose (MRD) of 600 mg/day.

When pregnant rats were given pregabalin (500, 1250, or 2500 mg/kg) orally throughout the period of organogenesis, incidences of specific skull alterations attributed to abnormally advanced ossification (premature fusion of the jugal and nasal sutures) were increased at ≥1250 mg/kg, and incidences of skeletal variations and retarded ossification were increased at all doses. Fetal body weights were decreased at the highest dose. The low dose in this study was associated with a plasma exposure (AUC) approximately 17 times human exposure at the MRD of 600 mg/day. A no-effect dose for rat embryo-fetal developmental toxicity was not established.

When pregnant rabbits were given LYRICA (250, 500, or 1250 mg/kg) orally throughout the period of organogenesis, decreased fetal body weight and increased incidences of skeletal malformations, visceral variations, and retarded ossification were observed at the highest dose. The no-effect dose for developmental toxicity in rabbits (500 mg/kg) was associated with a plasma exposure approximately 16 times human exposure at the MRD.

In a study in which female rats were dosed with LYRICA (50, 100, 250, 1250, or 2500 mg/kg) throughout gestation and lactation, offspring growth was reduced at ≥ 100 mg/kg and offspring survival was decreased at ≥250 mg/kg. The effect on offspring survival was pronounced at doses ≥1250 mg/kg, with 100% mortality in high-dose litters. When offspring were tested as adults, neurobehavioral abnormalities (decreased auditory startle responding) were observed at ≥250 mg/kg and reproductive impairment (decreased fertility and litter size) was seen at 1250 mg/kg. The no-effect dose for pre- and postnatal developmental toxicity in rats (50 mg/kg) produced a plasma exposure approximately 2 times human exposure at the MRD.

There are no adequate and well-controlled studies in pregnant women. Use LYRICA during pregnancy only if the potential benefit justifies the potential risk to the fetus.

To provide information regarding the effects of in utero exposure to LYRICA, physicians are advised to recommend that pregnant patients taking LYRICA enroll in the North American Antiepileptic Drug (NAAED) Pregnancy Registry. This can be done by calling the toll free number 1-888-233-2334, and must be done by patients themselves. Information on the registry can also be found at the website http://www.aedpregnancyregistry.org/.

8.2 Labor and Delivery

The effects of LYRICA on labor and delivery in pregnant women are unknown. In the prenatal-postnatal study in rats, pregabalin prolonged gestation and induced dystocia at exposures ≥50 times the mean human exposure (AUC (0–24) of 123 µg∙hr/mL) at the maximum recommended clinical dose of 600 mg/day.

8.3 Nursing Mothers

It is not known if pregabalin is excreted in human milk; it is, however, present in the milk of rats. Because many drugs are excreted in human milk, and because of the potential for tumorigenicity shown for pregabalin in animal studies, decide whether to discontinue nursing or to discontinue the drug, taking into account the importance of the drug to the mother.

8.4 Pediatric Use

The safety and efficacy of pregabalin in pediatric patients have not been established.

In studies in which pregabalin (50 to 500 mg/kg) was orally administered to young rats from early in the postnatal period (Postnatal Day 7) through sexual maturity, neurobehavioral abnormalities (deficits in learning and memory, altered locomotor activity, decreased auditory startle responding and habituation) and reproductive impairment (delayed sexual maturation and decreased fertility in males and females) were observed at doses ≥50 mg/kg. The neurobehavioral changes of acoustic startle persisted at ≥250 mg/kg and locomotor activity and water maze performance at ≥500 mg/kg in animals tested after cessation of dosing and, thus, were considered to represent long-term effects. The low effect dose for developmental neurotoxicity and reproductive impairment in juvenile rats (50 mg/kg) was associated with a plasma pregabalin exposure (AUC) approximately equal to human exposure at the maximum recommended dose of 600 mg/day. A no-effect dose was not established.

8.5 Geriatric Use

In controlled clinical studies of LYRICA in neuropathic pain associated with diabetic peripheral neuropathy, 246 patients were 65 to 74 years of age, and 73 patients were 75 years of age or older.

In controlled clinical studies of LYRICA in neuropathic pain associated with postherpetic neuralgia, 282 patients were 65 to 74 years of age, and 379 patients were 75 years of age or older.

In controlled clinical studies of LYRICA in epilepsy, there were only 10 patients 65 to 74 years of age, and 2 patients who were 75 years of age or older.

No overall differences in safety and efficacy were observed between these patients and younger patients.

In controlled clinical studies of LYRICA in fibromyalgia, 106 patients were 65 years of age or older. Although the adverse reaction profile was similar between the two age groups, the following neurological adverse reactions were more frequent in patients 65 years of age or older: dizziness, vision blurred, balance disorder, tremor, confusional state, coordination abnormal, and lethargy.

LYRICA is known to be substantially excreted by the kidney, and the risk of toxic reactions to LYRICA may be greater in patients with impaired renal function. Because LYRICA is eliminated primarily by renal excretion, adjust the dose for elderly patients with renal impairment [see Dosage and Administration (2.6)].

9 DRUG ABUSE AND DEPENDENCE

9.1 Controlled Substance

LYRICA is a Schedule V controlled substance.

LYRICA is not known to be active at receptor sites associated with drugs of abuse. As with any CNS active drug, carefully evaluate patients for history of drug abuse and observe them for signs of LYRICA misuse or abuse (e.g., development of tolerance, dose escalation, drug-seeking behavior).

9.2 Abuse

In a study of recreational users (N=15) of sedative/hypnotic drugs, including alcohol, LYRICA (450 mg, single dose) received subjective ratings of "good drug effect," "high" and "liking" to a degree that was similar to diazepam (30 mg, single dose). In controlled clinical studies in over 5500 patients, 4 % of LYRICA-treated patients and 1 % of placebo-treated patients overall reported euphoria as an adverse reaction, though in some patient populations studied, this reporting rate was higher and ranged from 1 to 12%.

9.3 Dependence

In clinical studies, following abrupt or rapid discontinuation of LYRICA, some patients reported symptoms including insomnia, nausea, headache or diarrhea [see Warnings and Precautions (5.8)], consistent with physical dependence. In the postmarketing experience, in addition to these reported symptoms there have also been reported cases of anxiety and hyperhidrosis.

10 OVERDOSAGE

Signs, Symptoms and Laboratory Findings of Acute Overdosage in Humans

There is limited experience with overdose of LYRICA. The highest reported accidental overdose of LYRICA during the clinical development program was 8000 mg, and there were no notable clinical consequences.

Treatment or Management of Overdose

There is no specific antidote for overdose with LYRICA. If indicated, elimination of unabsorbed drug may be attempted by emesis or gastric lavage; observe usual precautions to maintain the airway. General supportive care of the patient is indicated including monitoring of vital signs and observation of the clinical status of the patient. Contact a Certified Poison Control Center for up-to-date information on the management of overdose with LYRICA.

Although hemodialysis has not been performed in the few known cases of overdose, it may be indicated by the patient's clinical state or in patients with significant renal impairment. Standard hemodialysis procedures result in significant clearance of pregabalin (approximately 50% in 4 hours).

11 DESCRIPTION

Pregabalin is described chemically as (S)-3-(aminomethyl)-5-methylhexanoic acid. The molecular formula is C8H17NO2 and the molecular weight is 159.23. The chemical structure of pregabalin is:

Pregabalin is a white to off-white, crystalline solid with a pKa1 of 4.2 and a pKa2 of 10.6. It is freely soluble in water and both basic and acidic aqueous solutions. The log of the partition coefficient (n-octanol/0.05M phosphate buffer) at pH 7.4 is – 1.35.

LYRICA (pregabalin) Capsules are administered orally and are supplied as imprinted hard-shell capsules containing 75mg of pregabalin, along with lactose monohydrate, cornstarch, and talc as inactive ingredients. The capsule shells contain gelatin and titanium dioxide. In addition, the orange capsule shells contain red iron oxide and the white capsule shells contain sodium lauryl sulfate and colloidal silicon dioxide. Colloidal silicon dioxide is a manufacturing aid that may or may not be present in the capsule shells. The imprinting ink contains shellac, black iron oxide, propylene glycol, and potassium hydroxide.

12 CLINICAL PHARMACOLOGY

12.1 Mechanism of Action

LYRICA (pregabalin) binds with high affinity to the alpha2-delta site (an auxiliary subunit of voltage-gated calcium channels) in central nervous system tissues. Although the mechanism of action of pregabalin has not been fully elucidated, results with genetically modified mice and with compounds structurally related to pregabalin (such as gabapentin) suggest that binding to the alpha2-delta subunit may be involved in pregabalin's anti-nociceptive and antiseizure effects in animals. In animal models of nerve damage, pregabalin has been shown to reduce calcium-dependent release of pro-nociceptive neurotransmitters in the spinal cord, possibly by disrupting alpha2-delta containing-calcium channel trafficking and/or reducing calcium currents. Evidence from other animal models of nerve damage and persistent pain suggest the anti-nociceptive activities of pregabalin may also be mediated through interactions with descending noradrenergic and serotonergic pathways originating from the brainstem that modulate pain transmission in the spinal cord.

While pregabalin is a structural derivative of the inhibitory neurotransmitter gamma-aminobutyric acid (GABA), it does not bind directly to GABAA, GABAB, or benzodiazepine receptors, does not augment GABAA responses in cultured neurons, does not alter rat brain GABA concentration or have acute effects on GABA uptake or degradation. However, in cultured neurons prolonged application of pregabalin increases the density of GABA transporter protein and increases the rate of functional GABA transport. Pregabalin does not block sodium channels, is not active at opiate receptors, and does not alter cyclooxygenase enzyme activity. It is inactive at serotonin and dopamine receptors and does not inhibit dopamine, serotonin, or noradrenaline reuptake.

12.3 Pharmacokinetics

Pregabalin is well absorbed after oral administration, is eliminated largely by renal excretion, and has an elimination half-life of about 6 hours.

Absorption and Distribution

Following oral administration of LYRICA capsules under fasting conditions, peak plasma concentrations occur within 1.5 hours. Pregabalin oral bioavailability is ≥90% and is independent of dose. Following single- (25 to 300 mg) and multiple- dose (75 to 900 mg/day) administration, maximum plasma concentrations (Cmax) and area under the plasma concentration-time curve (AUC) values increase linearly. Following repeated administration, steady state is achieved within 24 to 48 hours. Multiple-dose pharmacokinetics can be predicted from single-dose data.

The rate of pregabalin absorption is decreased when given with food, resulting in a decrease in Cmax of approximately 25% to 30% and an increase in Tmax to approximately 3 hours. However, administration of pregabalin with food has no clinically relevant effect on the total absorption of pregabalin. Therefore, pregabalin can be taken with or without food.

Pregabalin does not bind to plasma proteins. The apparent volume of distribution of pregabalin following oral administration is approximately 0.5 L/kg. Pregabalin is a substrate for system L transporter which is responsible for the transport of large amino acids across the blood brain barrier. Although there are no data in humans, pregabalin has been shown to cross the blood brain barrier in mice, rats, and monkeys. In addition, pregabalin has been shown to cross the placenta in rats and is present in the milk of lactating rats.

Metabolism and Elimination

Pregabalin undergoes negligible metabolism in humans. Following a dose of radiolabeled pregabalin, approximately 90% of the administered dose was recovered in the urine as unchanged pregabalin. The N-methylated derivative of pregabalin, the major metabolite of pregabalin found in urine, accounted for 0.9% of the dose. In preclinical studies, pregabalin (S-enantiomer) did not undergo racemization to the R-enantiomer in mice, rats, rabbits, or monkeys.

Pregabalin is eliminated from the systemic circulation primarily by renal excretion as unchanged drug with a mean elimination half-life of 6.3 hours in subjects with normal renal function. Mean renal clearance was estimated to be 67.0 to 80.9 mL/min in young healthy subjects. Because pregabalin is not bound to plasma proteins this clearance rate indicates that renal tubular reabsorption is involved. Pregabalin elimination is nearly proportional to creatinine clearance (CLcr) [see Dosage and Administration, (2.6)].

Pharmacokinetics in Special Populations

Race

In population pharmacokinetic analyses of the clinical studies in various populations, the pharmacokinetics of LYRICA were not significantly affected by race (Caucasians, Blacks, and Hispanics).

Gender

Population pharmacokinetic analyses of the clinical studies showed that the relationship between daily dose and LYRICA drug exposure is similar between genders.

Renal Impairment and Hemodialysis

Pregabalin clearance is nearly proportional to creatinine clearance (CLcr). Dosage reduction in patients with renal dysfunction is necessary. Pregabalin is effectively removed from plasma by hemodialysis. Following a 4-hour hemodialysis treatment, plasma pregabalin concentrations are reduced by approximately 50%. For patients on hemodialysis, dosing must be modified [see Dosage and Administration (2.6)].

Elderly

Pregabalin oral clearance tended to decrease with increasing age. This decrease in pregabalin oral clearance is consistent with age-related decreases in CLcr. Reduction of pregabalin dose may be required in patients who have age-related compromised renal function [see Dosage and Administration, (2.6)].

Pediatric Pharmacokinetics

Pharmacokinetics of pregabalin have not been adequately studied in pediatric patients.

Drug Interactions

In Vitro Studies

Pregabalin, at concentrations that were, in general, 10-times those attained in clinical trials, does not inhibit human CYP1A2, CYP2A6, CYP2C9, CYP2C19, CYP2D6, CYP2E1, and CYP3A4 enzyme systems. In vitro drug interaction studies demonstrate that pregabalin does not induce CYP1A2 or CYP3A4 activity. Therefore, an increase in the metabolism of coadministered CYP1A2 substrates (e.g. theophylline, caffeine) or CYP 3A4 substrates (e.g., midazolam, testosterone) is not anticipated.

In Vivo Studies

The drug interaction studies described in this section were conducted in healthy adults, and across various patient populations.

Gabapentin

The pharmacokinetic interactions of pregabalin and gabapentin were investigated in 12 healthy subjects following concomitant single-dose administration of 100-mg pregabalin and 300-mg gabapentin and in 18 healthy subjects following concomitant multiple-dose administration of 200-mg pregabalin every 8 hours and 400-mg gabapentin every 8 hours. Gabapentin pharmacokinetics following single- and multiple-dose administration were unaltered by pregabalin coadministration. The extent of pregabalin absorption was unaffected by gabapentin coadministration, although there was a small reduction in rate of absorption.

Oral Contraceptive

Pregabalin coadministration (200 mg three times a day) had no effect on the steady-state pharmacokinetics of norethindrone and ethinyl estradiol (1 mg/35 µg, respectively) in healthy subjects.

Lorazepam

Multiple-dose administration of pregabalin (300 mg twice a day) in healthy subjects had no effect on the rate and extent of lorazepam single-dose pharmacokinetics and single-dose administration of lorazepam (1 mg) had no effect on the steady-state pharmacokinetics of pregabalin.

Oxycodone

Multiple-dose administration of pregabalin (300 mg twice a day) in healthy subjects had no effect on the rate and extent of oxycodone single-dose pharmacokinetics. Single-dose administration of oxycodone (10 mg) had no effect on the steady-state pharmacokinetics of pregabalin.

Ethanol

Multiple-dose administration of pregabalin (300 mg twice a day) in healthy subjects had no effect on the rate and extent of ethanol single-dose pharmacokinetics and single-dose administration of ethanol (0.7 g/kg) had no effect on the steady-state pharmacokinetics of pregabalin.

Phenytoin, carbamazepine, valproic acid, and lamotrigine

Steady-state trough plasma concentrations of phenytoin, carbamazepine and carbamazepine 10,11 epoxide, valproic acid, and lamotrigine were not affected by concomitant pregabalin (200 mg three times a day) administration.

Population pharmacokinetic analyses in patients treated with pregabalin and various concomitant medications suggest the following:

Therapeutic class | Specific concomitant drug studied
Concomitant drug has no effect on the pharmacokinetics of pregabalin
Hypoglycemics | Glyburide, insulin, metformin
Diuretics | Furosemide
Antiepileptic Drugs | Tiagabine
Concomitant drug has no effect on the pharmacokinetics of pregabalin and pregabalin has no effect on the pharmacokinetics of concomitant drug
Antiepileptic Drugs | Carbamazepine, lamotrigine, phenobarbital, phenytoin, topiramate, valproic acid

13 NONCLINICAL TOXICOLOGY

13.1 Carcinogenesis, Mutagenesis, Impairment of Fertility

Carcinogenesis

A dose-dependent increase in the incidence of malignant vascular tumors (hemangiosarcomas) was observed in two strains of mice (B6C3F1 and CD-1) given pregabalin (200, 1000, or 5000 mg/kg) in the diet for two years. Plasma pregabalin exposure (AUC) in mice receiving the lowest dose that increased hemangiosarcomas was approximately equal to the human exposure at the maximum recommended dose (MRD) of 600 mg/day. A no-effect dose for induction of hemangiosarcomas in mice was not established. No evidence of carcinogenicity was seen in two studies in Wistar rats following dietary administration of pregabalin for two years at doses (50, 150, or 450 mg/kg in males and 100, 300, or 900 mg/kg in females) that were associated with plasma exposures in males and females up to approximately 14 and 24 times, respectively, human exposure at the MRD.

Mutagenesis

Pregabalin was not mutagenic in bacteria or in mammalian cells in vitro, was not clastogenic in mammalian systems in vitro and in vivo, and did not induce unscheduled DNA synthesis in mouse or rat hepatocytes.

Impairment of Fertility

In fertility studies in which male rats were orally administered pregabalin (50 to 2500 mg/kg) prior to and during mating with untreated females, a number of adverse reproductive and developmental effects were observed. These included decreased sperm counts and sperm motility, increased sperm abnormalities, reduced fertility, increased preimplantation embryo loss, decreased litter size, decreased fetal body weights, and an increased incidence of fetal abnormalities. Effects on sperm and fertility parameters were reversible in studies of this duration (3–4 months). The no-effect dose for male reproductive toxicity in these studies (100 mg/kg) was associated with a plasma pregabalin exposure (AUC) approximately 3 times human exposure at the maximum recommended dose (MRD) of 600 mg/day.

In addition, adverse reactions on reproductive organ (testes, epididymides) histopathology were observed in male rats exposed to pregabalin (500 to 1250 mg/kg) in general toxicology studies of four weeks or greater duration. The no-effect dose for male reproductive organ histopathology in rats (250 mg/kg) was associated with a plasma exposure approximately 8 times human exposure at the MRD.

In a fertility study in which female rats were given pregabalin (500, 1250, or 2500 mg/kg) orally prior to and during mating and early gestation, disrupted estrous cyclicity and an increased number of days to mating were seen at all doses, and embryolethality occurred at the highest dose. The low dose in this study produced a plasma exposure approximately 9 times that in humans receiving the MRD. A no-effect dose for female reproductive toxicity in rats was not established.

Human Data

In a double-blind, placebo-controlled clinical trial to assess the effect of pregabalin on sperm motility, 30 healthy male subjects were exposed to pregabalin at a dose of 600 mg/day. After 3 months of treatment (one complete sperm cycle), the difference between placebo- and pregabalin-treated subjects in mean percent sperm with normal motility was <4% and neither group had a mean change from baseline of more than 2%. Effects on other male reproductive parameters in humans have not been adequately studied.

13.2 Animal Toxicology and/or Pharmacology

Dermatopathy

Skin lesions ranging from erythema to necrosis were seen in repeated-dose toxicology studies in both rats and monkeys. The etiology of these skin lesions is unknown. At the maximum recommended human dose (MRD) of 600 mg/day, there is a 2-fold safety margin for the dermatological lesions. The more severe dermatopathies involving necrosis were associated with pregabalin exposures (as expressed by plasma AUCs) of approximately 3 to 8 times those achieved in humans given the MRD. No increase in incidence of skin lesions was observed in clinical studies.

Ocular Lesions

Ocular lesions (characterized by retinal atrophy [including loss of photoreceptor cells] and/or corneal inflammation/mineralization) were observed in two lifetime carcinogenicity studies in Wistar rats. These findings were observed at plasma pregabalin exposures (AUC) ≥2 times those achieved in humans given the maximum recommended dose of 600 mg/day. A no-effect dose for ocular lesions was not established. Similar lesions were not observed in lifetime carcinogenicity studies in two strains of mice or in monkeys treated for 1 year.

14 CLINICAL STUDIES

14.1 Neuropathic Pain Associated with Diabetic Peripheral Neuropathy

The efficacy of the maximum recommended dose of LYRICA for the management of neuropathic pain associated with diabetic peripheral neuropathy was established in three double-blind, placebo-controlled, multicenter studies with three times a day dosing, two of which studied the maximum recommended dose. Patients were enrolled with either Type 1 or Type 2 diabetes mellitus and a diagnosis of painful distal symmetrical sensorimotor polyneuropathy for 1 to 5 years. A total of 89% of patients completed Studies DPN 1 and DPN 2. The patients had a minimum mean baseline pain score of ≥4 on an 11-point numerical pain rating scale ranging from 0 (no pain) to 10 (worst possible pain). The baseline mean pain scores across the two studies ranged from 6.1 to 6.7. Patients were permitted up to 4 grams of acetaminophen per day as needed for pain, in addition to pregabalin. Patients recorded their pain daily in a diary.

Study DPN 1: This 5-week study compared LYRICA 25, 100, or 200 mg three times a day with placebo. Treatment with LYRICA 100 and 200 mg three times a day statistically significantly improved the endpoint mean pain score and increased the proportion of patients with at least a 50% reduction in pain score from baseline. There was no evidence of a greater effect on pain scores of the 200 mg three times a day dose than the 100 mg three times a day dose, but there was evidence of dose dependent adverse reactions [see Adverse Reactions (6.1)]. For a range of levels of improvement in pain intensity from baseline to study endpoint, Figure 1 shows the fraction of patients achieving that level of improvement. The figure is cumulative, so that patients whose change from baseline is, for example, 50%, are also included at every level of improvement below 50%. Patients who did not complete the study were assigned 0% improvement. Some patients experienced a decrease in pain as early as Week 1, which persisted throughout the study.

Figure 1: Patients Achieving Various Levels of Improvement in Pain Intensity – Study DPN 1

Study DPN 2: This 8-week study compared LYRICA 100 mg three times a day with placebo. Treatment with LYRICA 100 mg three times a day statistically significantly improved the endpoint mean pain score and increased the proportion of patients with at least a 50% reduction in pain score from baseline. For various levels of improvement in pain intensity from baseline to study endpoint, Figure 2 shows the fraction of patients achieving that level of improvement. The figure is cumulative, so that patients whose change from baseline is, for example, 50%, are also included at every level of improvement below 50%. Patients who did not complete the study were assigned 0% improvement. Some patients experienced a decrease in pain as early as Week 1, which persisted throughout the study.

Figure 2: Patients Achieving Various Levels of Improvement in Pain Intensity– Study DPN 2

14.2 Postherpetic Neuralgia

The efficacy of LYRICA for the management of postherpetic neuralgia was established in three double-blind, placebo-controlled, multicenter studies. These studies enrolled patients with neuralgia persisting for at least 3 months following healing of herpes zoster rash and a minimum baseline score of ≥4 on an 11-point numerical pain rating scale ranging from 0 (no pain) to 10 (worst possible pain). Seventy-three percent of patients completed the studies. The baseline mean pain scores across the 3 studies ranged from 6 to 7. Patients were permitted up to 4 grams of acetaminophen per day as needed for pain, in addition to pregabalin. Patients recorded their pain daily in a diary.

Study PHN 1: This 13-week study compared LYRICA 75, 150, and 300 mg twice daily with placebo. Patients with creatinine clearance (CLcr) between 30 to 60 mL/min were randomized to 75 mg, 150 mg, or placebo twice daily. Patients with creatinine clearance greater than 60 mL/min were randomized to 75 mg, 150 mg, 300 mg or placebo twice daily. In patients with creatinine clearance greater than 60 mL/min treatment with all doses of LYRICA statistically significantly improved the endpoint mean pain score and increased the proportion of patients with at least a 50% reduction in pain score from baseline. Despite differences in dosing based on renal function, patients with creatinine clearance between 30 to 60 mL/min tolerated LYRICA less well than patients with creatinine clearance greater than 60 mL/min as evidenced by higher rates of discontinuation due to adverse reactions. For various levels of improvement in pain intensity from baseline to study endpoint, Figure 3 shows the fraction of patients achieving that level of improvement. The figure is cumulative, so that patients whose change from baseline is, for example, 50%, are also included at every level of improvement below 50%. Patients who did not complete the study were assigned 0% improvement. Some patients experienced a decrease in pain as early as Week 1, which persisted throughout the study.

Figure 3: Patients Achieving Various Levels of Improvement in Pain Intensity– Study PHN 1

Study PHN 2: This 8-week study compared LYRICA 100 or 200 mg three times a day with placebo, with doses assigned based on creatinine clearance. Patients with creatinine clearance between 30 to 60 mL/min were treated with 100 mg three times a day, and patients with creatinine clearance greater than 60 mL/min were treated with 200 mg three times daily. Treatment with LYRICA statistically significantly improved the endpoint mean pain score and increased the proportion of patients with at least a 50% reduction in pain score from baseline. For various levels of improvement in pain intensity from baseline to study endpoint, Figure 4 shows the fraction of patients achieving those levels of improvement. The figure is cumulative, so that patients whose change from baseline is, for example, 50%, are also included at every level of improvement below 50%. Patients who did not complete the study were assigned 0% improvement. Some patients experienced a decrease in pain as early as Week 1, which persisted throughout the study.

Figure 4: Patients Achieving Various Levels of Improvement in Pain Intensity – Study PHN 2

Study PHN 3: This 8-week study compared LYRICA 50 or 100 mg three times a day with placebo with doses assigned regardless of creatinine clearance. Treatment with LYRICA 50 and 100 mg three times a day statistically significantly improved the endpoint mean pain score and increased the proportion of patients with at least a 50% reduction in pain score from baseline. Patients with creatinine clearance between 30 to 60 mL/min tolerated LYRICA less well than patients with creatinine clearance greater than 60 mL/min as evidenced by markedly higher rates of discontinuation due to adverse reactions. For various levels of improvement in pain intensity from baseline to study endpoint, Figure 5 shows the fraction of patients achieving that level of improvement. The figure is cumulative, so that patients whose change from baseline is, for example, 50%, are also included at every level of improvement below 50%. Patients who did not complete the study were assigned 0% improvement. Some patients experienced a decrease in pain as early as Week 1, which persisted throughout the study.

Figure 5: Patients Achieving Various Levels of Improvement in Pain Intensity– Study PHN 3

14.3 Adjunctive Therapy for Adult Patients with Partial Onset Seizures

The efficacy of LYRICA as adjunctive therapy in partial onset seizures was established in three 12-week, randomized, double-blind, placebo-controlled, multicenter studies in adult patients. Patients were enrolled who had partial onset seizures with or without secondary generalization and were not adequately controlled with 1 to 3 concomitant antiepileptic drugs (AEDs). Patients taking gabapentin were required to discontinue gabapentin treatment 1 week prior to entering baseline. During an 8-week baseline period, patients had to experience at least 6 partial onset seizures with no seizure-free period exceeding 4 weeks. The mean duration of epilepsy was 25 years in these 3 studies and the mean and median baseline seizure frequencies were 22.5 and 10 seizures per month, respectively. Approximately half of the patients were taking 2 concurrent AEDs at baseline. Among the LYRICA-treated patients, 80% completed the double-blind phase of the studies.

Table 8 shows median baseline seizure rates and median percent reduction in seizure frequency by dose.

Table 8. Seizure Response in Controlled, Add-On Epilepsy Studies
Daily Dose of Pregabalin | Dosing Regimen | N | Baseline Seizure Frequency/mo | Median % Change from Baseline | p-value, vs. placebo
Study E1
Placebo | BID | 100 | 9.5 | 0
50 mg/day | BID | 88 | 10.3 | -9 | 0.4230
150 mg/day | BID | 86 | 8.8 | -35 | 0.0001
300 mg/day | BID | 90 | 9.8 | -37 | 0.0001
600 mg/day | BID | 89 | 9.0 | -51 | 0.0001
Study E2
Placebo | TID | 96 | 9.3 | 1
150 mg/day | TID | 99 | 11.5 | -17 | 0.0007
600 mg/day | TID | 92 | 12.3 | -43 | 0.0001
Study E3
Placebo | BID/TID | 98 | 11 | -1
600 mg/day | BID | 103 | 9.5 | -36 | 0.0001
600 mg/day | TID | 111 | 10 | -48 | 0.0001

In the first study (E1), there was evidence of a dose-response relationship for total daily doses of Lyrica between 150 and 600 mg/day; a dose of 50 mg/day was not effective. In the first study (E1), each daily dose was divided into two equal doses (twice a day dosing). In the second study (E2), each daily dose was divided into three equal doses (three times a day dosing). In the third study (E3), the same total daily dose was divided into two equal doses for one group (twice a day dosing) and three equal doses for another group (three times a day dosing). While the three times a day dosing group in Study E3 performed numerically better than the twice a day dosing group, this difference was small and not statistically significant.

A secondary outcome measure included the responder rate (proportion of patients with ≥50% reduction from baseline in partial seizure frequency). The following figure displays responder rate by dose for two of the studies.

Figure 6: Responder rate by add-on epilepsy study

Figure 7: Seizure Reduction by Dose (All Partial Onset Seizures) for Studies E1, E2, and E3

Subset evaluations of the antiseizure efficacy of LYRICA showed no clinically important differences as a function of age, gender, or race.

14.4 Management of Fibromyalgia

The efficacy of LYRICA for management of fibromyalgia was established in one 14-week, double-blind, placebo-controlled, multicenter study (F1) and one six-month, randomized withdrawal study (F2). Studies F1 and F2 enrolled patients with a diagnosis of fibromyalgia using the American College of Rheumatology (ACR) criteria (history of widespread pain for 3 months, and pain present at 11 or more of the 18 specific tender point sites). The studies showed a reduction in pain by visual analog scale. In addition, improvement was demonstrated based on a patient global assessment (PGIC), and on the Fibromyalgia Impact Questionnaire (FIQ).

Study F1: This 14-week study compared LYRICA total daily doses of 300 mg, 450 mg and 600 mg with placebo. Patients were enrolled with a minimum mean baseline pain score of greater than or equal to 4 on an 11-point numeric pain rating scale and a score of greater than or equal to 40 mm on the 100 mm pain visual analog scale (VAS). The baseline mean pain score in this trial was 6.7. Responders to placebo in an initial one-week run-in phase were not randomized into subsequent phases of the study. A total of 64% of patients randomized to LYRICA completed the study. There was no evidence of a greater effect on pain scores of the 600 mg daily dose than the 450 mg daily dose, but there was evidence of dose-dependent adverse reactions [see Adverse Reactions (6.1)]. Some patients experienced a decrease in pain as early as Week 1, which persisted throughout the study. The results are summarized in Figure 8 and Table 9.

For various levels of improvement in pain intensity from baseline to study endpoint, Figure 8 shows the fraction of patients achieving that level of improvement. The figure is cumulative. Patients who did not complete the study were assigned 0% improvement. Some patients experienced a decrease in pain as early as Week 1, which persisted throughout the study.

Figure 8: Patients Achieving Various Levels of Improvement in Pain Intensity – Fibromyalgia Study F1

Table 9. Patient Global Response in Fibromyalgia Study F1
Patient Global Impression of Change
Treatment Group (mg/day) | % Any Improvement | 95% CI
Placebo | 47.6 | (40.0,55.2)
PGB 300 | 68.1 | (60.9, 75.3)
PGB 450 | 77.8 | (71.5, 84.0)
PGB 600 | 66.1 | (59.1, 73.1)
PGB = Pregabalin

Study F2: This randomized withdrawal study compared LYRICA with placebo. Patients were titrated during a 6-week open-label dose optimization phase to a total daily dose of 300 mg, 450 mg, or 600 mg. Patients were considered to be responders if they had both: 1) at least a 50% reduction in pain (VAS) and, 2) rated their overall improvement on the PGIC as "much improved" or "very much improved." Those who responded to treatment were then randomized in the double-blind treatment phase to either the dose achieved in the open-label phase or to placebo. Patients were treated for up to 6 months following randomization. Efficacy was assessed by time to loss of therapeutic response, defined as 1) less than 30% reduction in pain (VAS) from open-label baseline during two consecutive visits of the double-blind phase, or 2) worsening of FM symptoms necessitating an alternative treatment. Fifty-four percent of patients were able to titrate to an effective and tolerable dose of LYRICA during the 6-week open-label phase. Of the patients entering the randomized treatment phase assigned to remain on LYRICA, 38% of patients completed 26 weeks of treatment versus 19% of placebo-treated patients.

When considering return of pain or withdrawal due to adverse events as loss of response (LTR), treatment with LYRICA resulted in a longer time to loss of therapeutic response than treatment with placebo. Fifty-three percent of the pregabalin-treated subjects compared to 33% of placebo patients remained on study drug and maintained a therapeutic response to Week 26 of the study. Treatment with LYRICA also resulted in a longer time to loss of response based on the FIQ [Time to worsening of the FIQ was defined as the time to a 1-point increase from double-blind baseline in each of the subscales, and a 5-point increase from double-blind baseline evaluation for the FIQ total score.] , and longer time to loss of overall assessment of patient status, as measured by the PGIC [Time to PGIC lack of improvement was defined as time to PGIC assessments indicating less improvement than "much improvement."] .

Figure 9: Time to Loss of Therapeutic Response, Fibromyalgia Study F2 (Kaplan-Meier Analysis)

14.5 Management of Neuropathic Pain Associated with Spinal Cord Injury

The efficacy of LYRICA for the management of neuropathic pain associated with spinal cord injury was established in two double-blind, placebo-controlled, multicenter studies. Patients were enrolled with neuropathic pain associated with spinal cord injury that persisted continuously for at least three months or with relapses and remissions for at least six months. A total of 63% of patients completed study 1 and 84% completed study 2. The patients had a minimum mean baseline pain score of ≥4 on an 11-point numerical pain rating scale ranging from 0 (no pain) to 10 (worst possible pain). The baseline mean pain scores across the two studies ranged from 6.5 to 6.7.

Patients were allowed to take opioids, non-opioid analgesics, antiepileptic drugs, muscle relaxants, and antidepressant drugs if the dose was stable for 30 days prior to screening. Patients were allowed to take acetaminophen and nonsteroidal anti-inflammatory drugs during the studies.

Study SCI 1: This 12-week, randomized, double-blind, parallel-group, multicenter, flexible dose (150–600 mg/day) study compared pregabalin with placebo. The 12-week study consisted of a 3-week dose adjustment phase and a 9-week dose maintenance phase. Treatment with LYRICA 150–600 mg/day statistically significantly improved the endpoint weekly mean pain score, and increased the proportion of patients with at least a 30% and 50% reduction in pain score from baseline. The fraction of patients achieving various levels of improvement in pain intensity from baseline to Week 12 is presented in Figure 10. Some patients experienced a decrease in pain as early as week 1, which persisted throughout the study.

Figure 10: Patients Achieving Various Levels of Improvement in Pain Intensity – Study SCI 1

Study SCI 2: This 16-week, randomized, double-blind, placebo-controlled, parallel-group, multicenter, flexible dose (150–600 mg/day, in increments of 150 mg) study compared the efficacy, safety and tolerability of pregabalin with placebo. The 16-week study consisted of a 4-week dose adjustment phase and a 12-week dose maintenance phase. Treatment with LYRICA statistically significantly improved the endpoint weekly mean pain score, and increased the proportion of patients with at least a 30% and 50% reduction in pain score from baseline. The fraction of patients achieving various levels of improvement in pain intensity from baseline to Week 16 is presented in Figure 11. Some patients experienced a decrease in pain as early as week 1, which persisted throughout the study.

Figure 11: Patients Achieving Various Levels of Improvement in Pain Intensity – Study SCI 2

16 HOW SUPPLIED/STORAGE AND HANDLING

75 mg capsules:

White/orange hard gelatin capsule printed with black ink "Pfizer" on the cap, "PGN 75" on the body; available in:

Bottles of 90: NDC 68258-7980-09

Storage and Handling

Store at 25°C (77°F); excursions permitted to 15°C to 30°C (59°F to 86°F) (see USP Controlled Room Temperature).

See FDA-Approved Medication Guide

17 PATIENT COUNSELING INFORMATION

17.1 Medication Guide

Inform patients of the availability of a Medication Guide, and instruct them to read the Medication Guide prior to taking LYRICA. Instruct patients to take LYRICA only as prescribed.

17.2 Angioedema

Advise patients that LYRICA may cause angioedema, with swelling of the face, mouth (lip, gum, tongue) and neck (larynx and pharynx) that can lead to life-threatening respiratory compromise. Instruct patients to discontinue LYRICA and immediately seek medical care if they experience these symptoms [see Warnings and Precautions (5.1)].

17.3 Hypersensitivity

Advise patients that LYRICA has been associated with hypersensitivity reactions such as wheezing, dyspnea, rash, hives, and blisters. Instruct patients to discontinue LYRICA and immediately seek medical care if they experience these symptoms [see Warnings and Precautions (5.2)].

17.4 Suicidal Thinking and Behavior

Patients, their caregivers, and families should be counseled that AEDs, including LYRICA, may increase the risk of suicidal thoughts and behavior and should be advised of the need to be alert for the emergence or worsening of symptoms of depression, any unusual changes in mood or behavior, or the emergence of suicidal thoughts, behavior, or thoughts about self-harm. Report behaviors of concern immediately to healthcare providers [see Warnings and Precautions (5.4)].

17.5 Dizziness and Somnolence

Counsel patients that LYRICA may cause dizziness, somnolence, blurred vision and other CNS signs and symptoms. Accordingly, advise patients not to drive, operate complex machinery, or engage in other hazardous activities until they have gained sufficient experience on LYRICA to gauge whether or not it affects their mental, visual, and/or motor performance adversely. [see Warnings and Precautions (5.6)].

17.6 Weight Gain and Edema

Counsel patients that LYRICA may cause edema and weight gain. Advise patients that concomitant treatment with LYRICA and a thiazolidinedione antidiabetic agent may lead to an additive effect on edema and weight gain. For patients with preexisting cardiac conditions, this may increase the risk of heart failure. [see Warnings and Precautions (5.5 and 5.7)].

17.7 Abrupt or Rapid Discontinuation

Advise patients to take LYRICA as prescribed. Abrupt or rapid discontinuation may result in insomnia, nausea, headache, anxiety, hyperhidrosis, or diarrhea. [see Warnings and Precautions (5.8)].

17.8 Ophthalmological Effects

Counsel patients that LYRICA may cause visual disturbances. Inform patients that if changes in vision occur, they should notify their physician [see Warnings and Precautions (5.10)].

17.9 Creatine Kinase Elevations

Instruct patients to promptly report unexplained muscle pain, tenderness, or weakness, particularly if accompanied by malaise or fever. [see Warnings and Precautions (5.11)].

17.10 CNS Depressants

Inform patients who require concomitant treatment with central nervous system depressants such as opiates or benzodiazepines that they may experience additive CNS side effects, such as somnolence [see Warnings and Precautions (5.6) and Drug Interactions (7)].

17.11 Alcohol

Tell patients to avoid consuming alcohol while taking LYRICA, as LYRICA may potentiate the impairment of motor skills and sedating effects of alcohol.

17.12 Use in Pregnancy

Instruct patients to notify their physician if they become pregnant or intend to become pregnant during therapy, and to notify their physician if they are breast feeding or intend to breast feed during therapy [see Use In Specific Populations (8.1) and (8.3)].

Encourage patients to enroll in the NAAED Pregnancy Registry if they become pregnant. This registry is collecting information about the safety of antiepileptic drugs during pregnancy. To enroll, patients can call the toll free number 1-888-233-2334 [see Use In Specific Populations (8.1)].

17.13 Male Fertility

Inform men being treated with LYRICA who plan to father a child of the potential risk of male-mediated teratogenicity. In preclinical studies in rats, pregabalin was associated with an increased risk of male-mediated teratogenicity. The clinical significance of this finding is uncertain [see Nonclinical Toxicology (13.1)].

17.14 Dermatopathy

Instruct diabetic patients to pay particular attention to skin integrity while being treated with LYRICA. Some animals treated with pregabalin developed skin ulcerations, although no increased incidence of skin lesions associated with LYRICA was observed in clinical trials [see Nonclinical Toxicology (13.2)].

LAB-0294-23.0

MEDICATION GUIDE

LYRICA (LEER-i-kah)
(pregabalin)
Capsules and Oral Solution, CV

Read this Medication Guide before you start taking LYRICA and each time you get a refill. There may be new information. This information does not take the place of talking to your healthcare provider about your medical condition or treatment. If you have any questions about LYRICA, ask your healthcare provider or pharmacist.

What is the most important information I should know about LYRICA?

LYRICA may cause serious side effects including:

- Serious, even life-threatening, allergic reactions
- Suicidal thoughts or actions
- Swelling of your hands, legs and feet
- Dizziness and sleepiness

These serious side effects are described below:

1. Serious, even life-threatening, allergic reactions.
  Stop taking LYRICA and call your healthcare provider right away if you have any of these signs of a serious allergic reaction:
  - swelling of your face, mouth, lips, gums, tongue, throat or neck
  - trouble breathing
  - rash, hives (raised bumps) or blisters

2. Like other antiepileptic drugs, LYRICA may cause suicidal thoughts or actions in a very small number of people, about 1 in 500.
  Call a healthcare provider right away if you have any of these symptoms, especially if they are new, worse, or worry you:
  - thoughts about suicide or dying
  - attempts to commit suicide
  - new or worse depression
  - new or worse anxiety
  - feeling agitated or restless
  - panic attacks
  - trouble sleeping (insomnia)
  - new or worse irritability
  - acting aggressive, being angry, or violent
  - acting on dangerous impulses
  - an extreme increase in activity and talking (mania)
  - other unusual changes in behavior or mood
  If you have suicidal thoughts or actions, do not stop LYRICA without first talking to a healthcare provider.
  - Stopping LYRICA suddenly can cause serious problems.
  - Suicidal thoughts or actions can be caused by things other than medicines. If you have suicidal thoughts or actions, your healthcare provider may check for other causes.
  How can I watch for early symptoms of suicidal thoughts and actions?
  - Pay attention to any changes, especially sudden changes, in mood, behaviors, thoughts, or feelings.
  - Keep all follow-up visits with your healthcare provider as scheduled.
  - Call your healthcare provider between visits as needed, especially if you are worried about symptoms.

3. Swelling of your hands, legs and feet. This swelling can be a serious problem for people with heart problems.

4. Dizziness and sleepiness.
  Do not drive a car, work with machines, or do other dangerous activities until you know how LYRICA affects you. Ask your healthcare provider about when it will be okay to do these activities.

What is LYRICA?

LYRICA is a prescription medicine used in adults, 18 years and older, to treat:

- pain from damaged nerves (neuropathic pain) that happens with diabetes
- pain from damaged nerves (neuropathic pain) that follows healing of shingles
- partial seizures when taken together with other seizure medicines
- fibromyalgia (pain all over your body)
- pain from damaged nerves (neuropathic pain) that follows spinal cord injury

LYRICA has not been studied in children under 18 years of age.

Who Should Not Take LYRICA?

Do not take LYRICA if you are allergic to pregabalin or any of the ingredients in LYRICA.

See "What is the most important information I should know about LYRICA?" for the signs of an allergic reaction.

See the end of this leaflet for a complete list of ingredients in LYRICA.

What should I tell my healthcare provider before taking LYRICA?

Before taking LYRICA, tell your healthcare provider about all your medical conditions, including if you:

- have or have had depression, mood problems or suicidal thoughts or behavior
- have kidney problems or get kidney dialysis
- have heart problems including heart failure
- have a bleeding problem or a low blood platelet count
- have abused prescription medicines, street drugs, or alcohol in the past
- have ever had swelling of your face, mouth, tongue, lips, gums, neck, or throat (angioedema)
- plan to father a child. Animal studies have shown that pregabalin, the active ingredient in LYRICA, made male animals less fertile and caused sperm to change. Also, in animal studies, birth defects were seen in the offspring (babies) of male animals treated with pregabalin. It is not known if these problems can happen in people who take LYRICA.
- are pregnant or plan to become pregnant. It is not known if LYRICA will harm your unborn baby. You and your healthcare provider will have to decide if you should take LYRICA while you are pregnant. If you become pregnant while taking LYRICA, talk to your healthcare provider about registering with the North American Antiepileptic Drug Pregnancy Registry. You can enroll in this registry by calling 1-888-233-2334. The purpose of this registry is to collect information about the safety of antiepileptic drugs during pregnancy.
- are breastfeeding. It is not known if LYRICA passes into breast milk and if it can harm your baby. You and your healthcare provider should discuss whether you should take LYRICA or breast-feed, but you should not do both

Tell your healthcare provider about all the medicines you take including prescription and non-prescription medicines, vitamins or herbal supplements. LYRICA and other medicines may affect each other causing side effects. Especially tell your healthcare provider if you take:

- angiotensin converting enzyme (ACE) inhibitors, which are used to treat many conditions, including high blood pressure. You may have a higher chance for swelling and hives if these medicines are taken with LYRICA. See "What is the most important information I should know about LYRICA?"
- Avandia (rosiglitazone), Avandamet (contains rosiglitazone and metformin), or Actos (pioglitazone) for diabetes. You may have a higher chance of weight gain or swelling of your hands or feet if these medicines are taken with LYRICA. See "What are the possible side effects of LYRICA."
- any narcotic pain medicine (such as oxycodone), tranquilizers or medicines for anxiety (such as lorazepam). You may have a higher chance for dizziness and sleepiness if these medicines are taken with LYRICA.
- any medicines that make you sleepy

Know the medicines you take. Keep a list of them with you to show your healthcare provider and pharmacist each time you get a new medicine. Do not start a new medicine without talking with your healthcare provider.

How should I take LYRICA?

- Take LYRICA exactly as prescribed. Your healthcare provider will tell you how much LYRICA to take and when to take it. Take LYRICA at the same times each day.
- LYRICA may be taken with or without food.
- Your healthcare provider may change your dose. Do not change your dose without talking to your healthcare provider.
- Do not stop taking LYRICA without talking to your healthcare provider. If you stop taking LYRICA suddenly you may have headaches, nausea, diarrhea, trouble sleeping, increased sweating, or you may feel anxious. If you have epilepsy and you stop taking LYRICA suddenly, you may have seizures more often. Talk with your healthcare provider about how to stop LYRICA slowly.
- If you miss a dose, take it as soon as you remember. If it is almost time for your next dose, just skip the missed dose. Take the next dose at your regular time. Do not take two doses at the same time.
- If you take too much LYRICA, call your healthcare provider or poison control center, or go to the nearest emergency room right away.

What should I avoid while taking LYRICA?

- Do not drive a car, work with machines, or do other dangerous activities until you know how LYRICA affects you.
- Do not drink alcohol while taking LYRICA. LYRICA and alcohol can affect each other and increase side effects such as sleepiness and dizziness.

What are the possible side effects of LYRICA?

LYRICA may cause serious side effects, including:

- See "What is the most important information I should know about LYRICA?"
- muscle problems, muscle pain, soreness, or weakness. If you have these symptoms, especially if you feel sick and have a fever, tell your healthcare provider right away.
- problems with your eyesight, including blurry vision. Call your healthcare provider if you have any changes in your eyesight.
- weight gain. If you have diabetes, weight gain may affect the management of your diabetes. Weight gain can also be a serious problem for people with heart problems.
- feeling "high"

The most common side effects of LYRICA are:

- dizziness
- blurry vision
- weight gain
- sleepiness
- trouble concentrating
- swelling of hands and feet
- dry mouth

LYRICA caused skin sores in animal studies. Skin sores did not happen in studies in people. If you have diabetes, you should pay attention to your skin while taking LYRICA and tell your healthcare provider about any sores or skin problems.

Tell your healthcare provider about any side effect that bothers you or that does not go away.

These are not all the possible side effects of LYRICA. For more information, ask your healthcare provider or pharmacist.

Call your doctor for medical advice about side effects. You may report side effects to FDA at 1-800-FDA-1088.

How should I store LYRICA?

- Store LYRICA capsules and oral solution at room temperature, 59°F to 86°F (15°C to 30°C) in its original package.
- Safely throw away any LYRICA that is out of date or no longer needed.
- Keep LYRICA and all medicines out of the reach of children.

General information about LYRICA

Medicines are sometimes prescribed for purposes other than those listed in a Medication Guide. Do not use LYRICA for a condition for which it was not prescribed. Do not give LYRICA to other people, even if they have the same symptoms you have. It may harm them.

This Medication Guide summarizes the most important information about LYRICA. If you would like more information, talk with your healthcare provider. You can ask your healthcare provider or pharmacist for information about LYRICA that is written for health professionals.

You can also visit the LYRICA website at www.LYRICA.com or call 1-866-459-7422 (1-866-4LYRICA).

What are the ingredients In LYRICA?

Active ingredient: pregabalin

Inactive ingredients:

LYRICA capsules: lactose monohydrate, cornstarch, talc

Capsule shell: gelatin and titanium dioxide; Orange capsule shell: red iron oxide; White capsule shell: sodium lauryl sulfate, colloidal silicon dioxide. Colloidal silicon dioxide is a manufacturing aid that may or may not be present in the capsule shells.

Imprinting ink: shellac, black iron oxide, propylene glycol, potassium hydroxide.

LYRICA oral solution: methylparaben, propylparaben, monobasic sodium phosphate anhydrous, dibasic sodium phosphate anhydrous, sucralose, artificial strawberry #11545 and purified water.

This Medication Guide has been approved by the U.S. Food and Drug Administration.

LAB-0299-12.0

06/2013

PACKAGE LABEL

PRINCIPAL DISPLAY PANEL

ALWAYS DISPENSE WITH MEDICATION GUIDE

NDC 68258-7980-XX

NDC 68258-7980-09